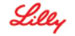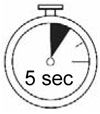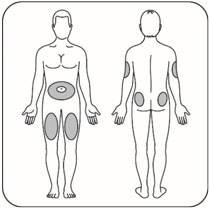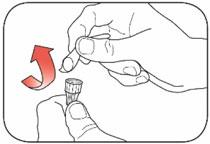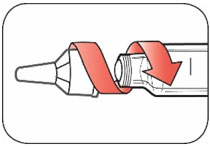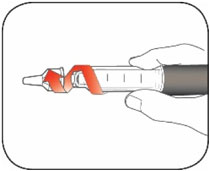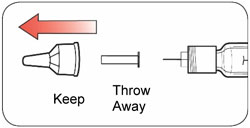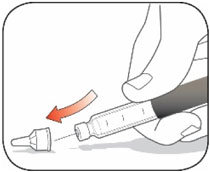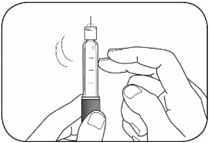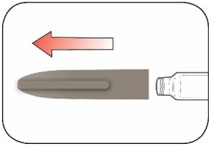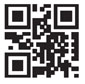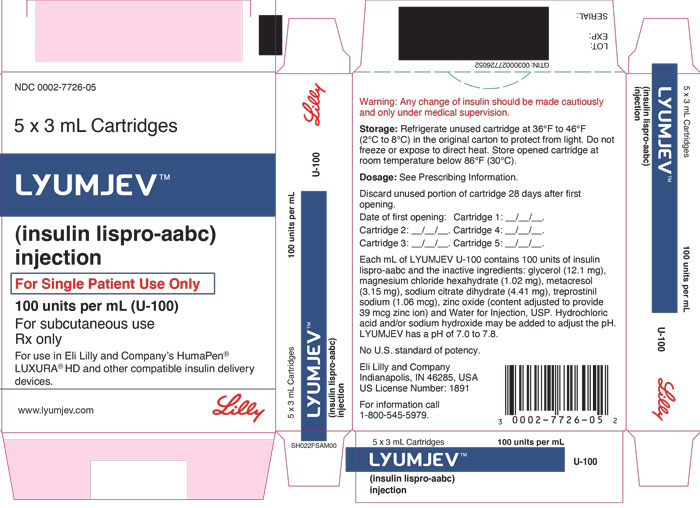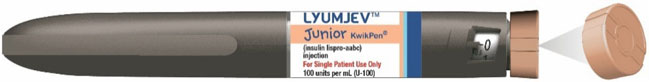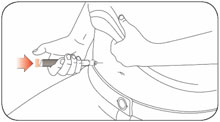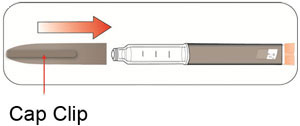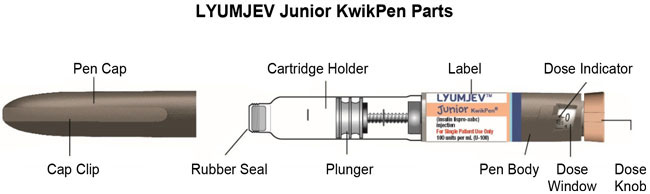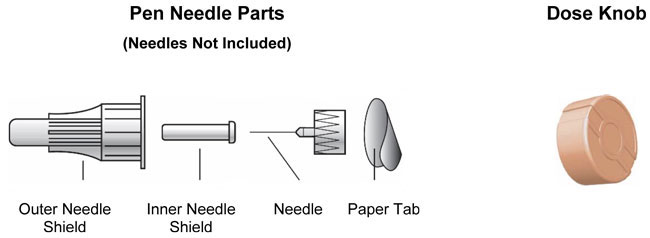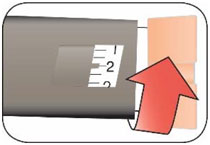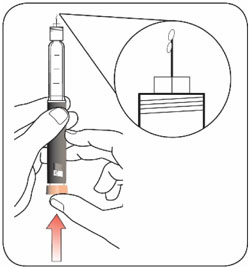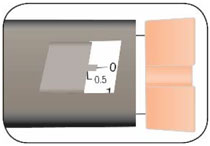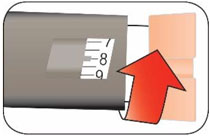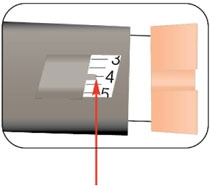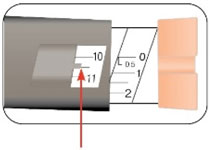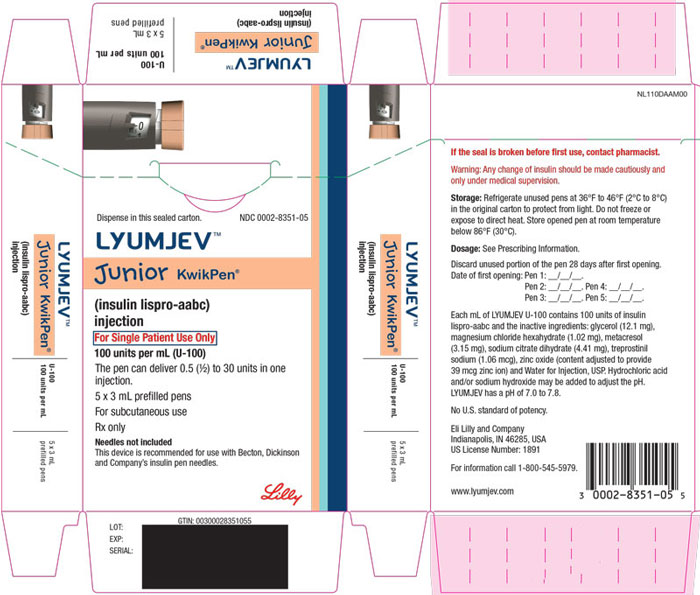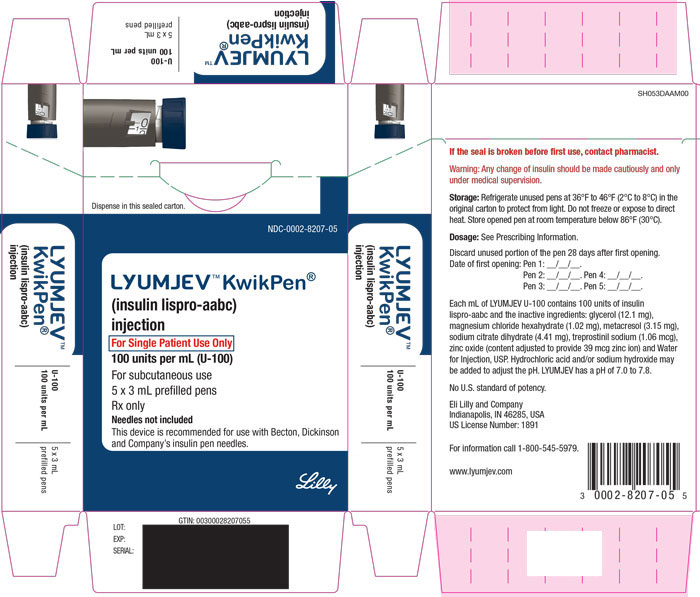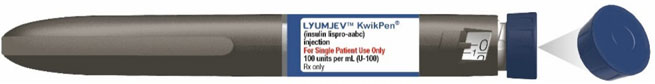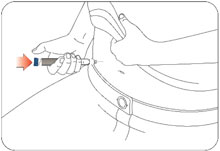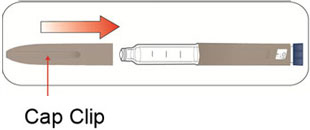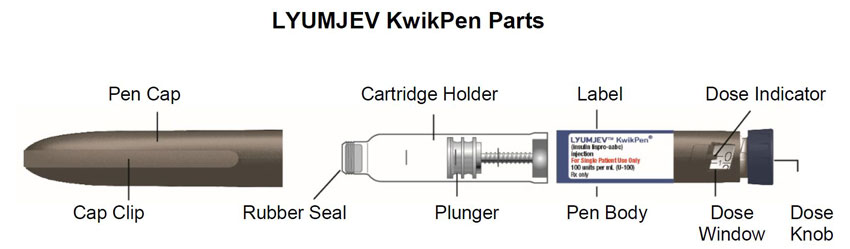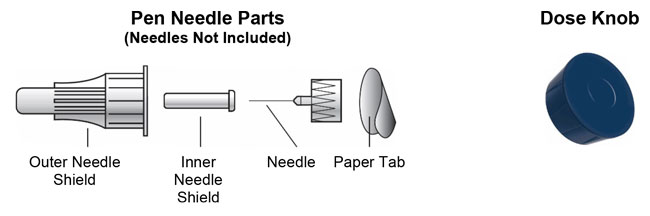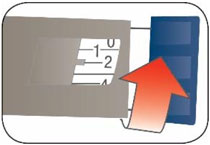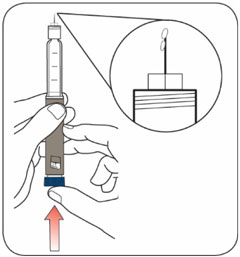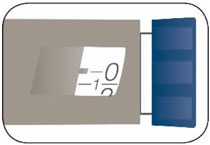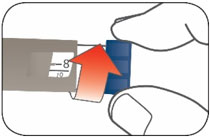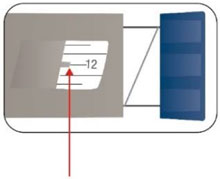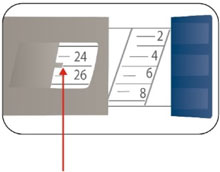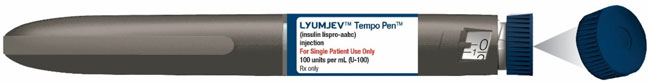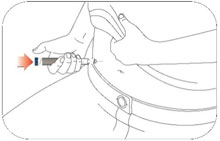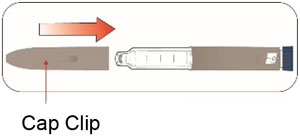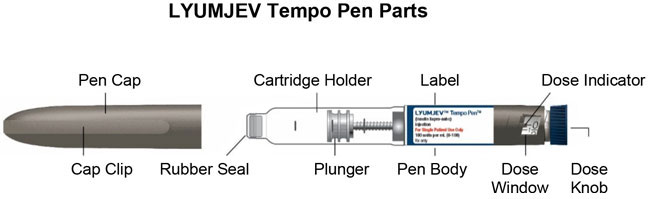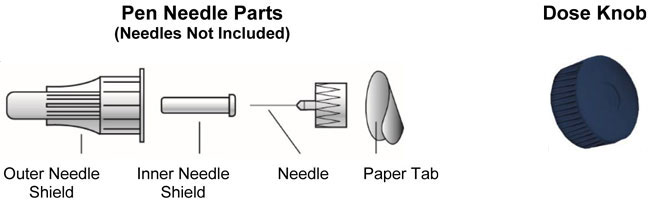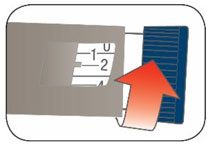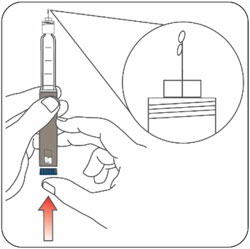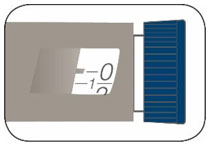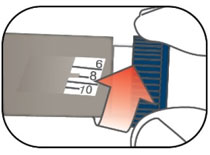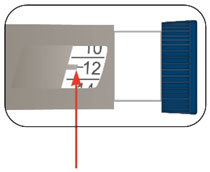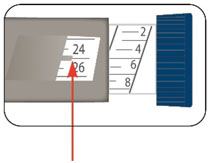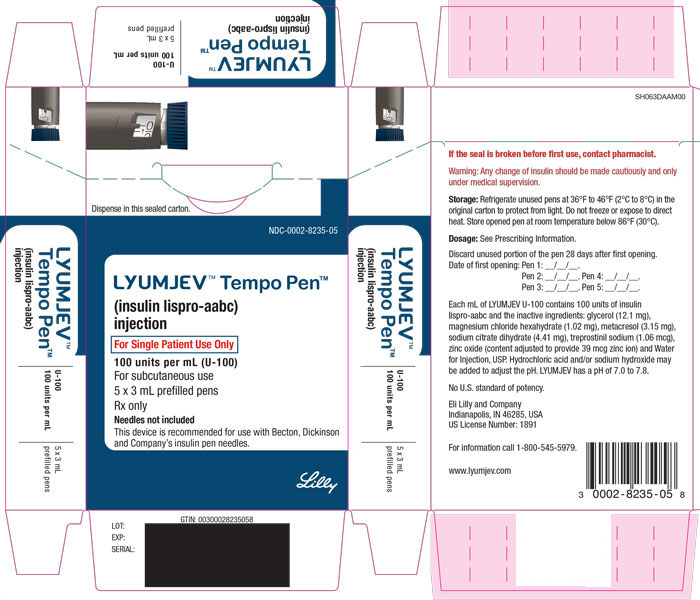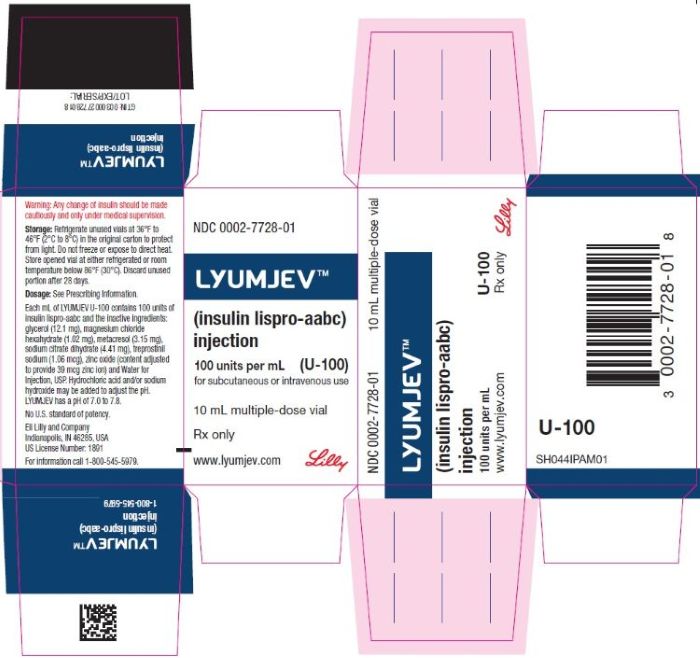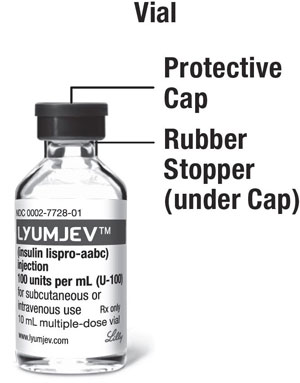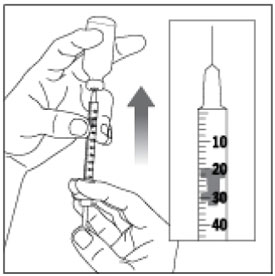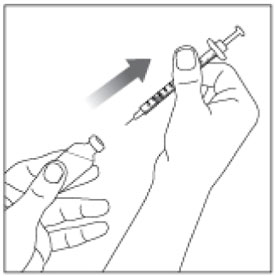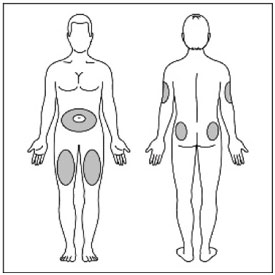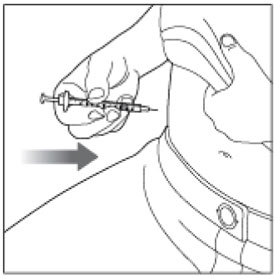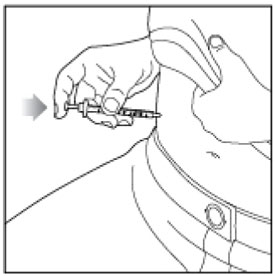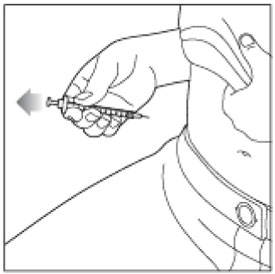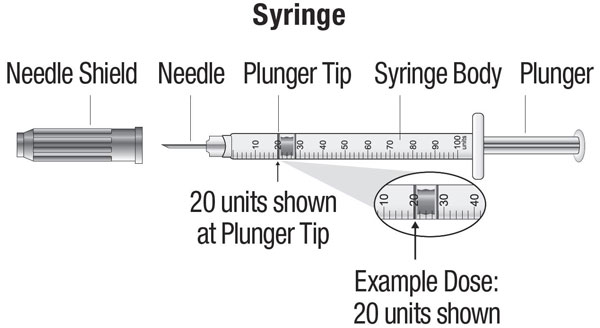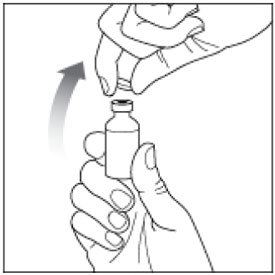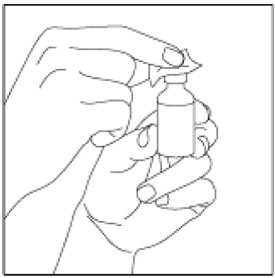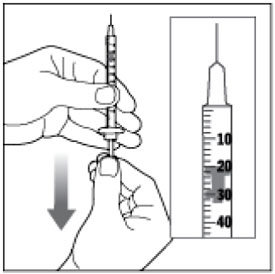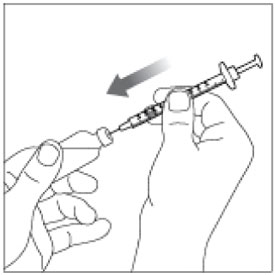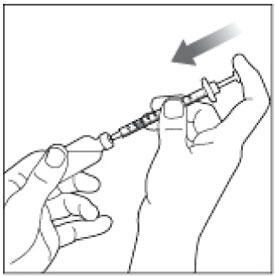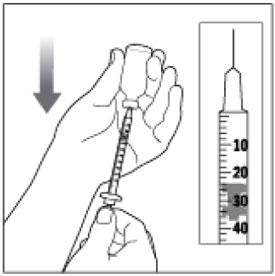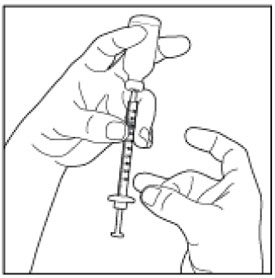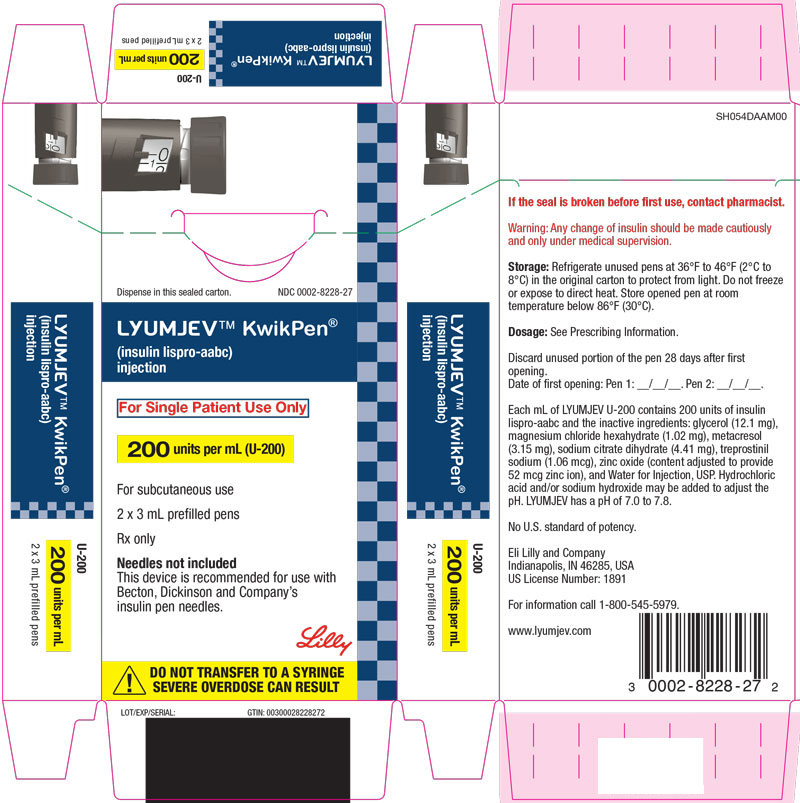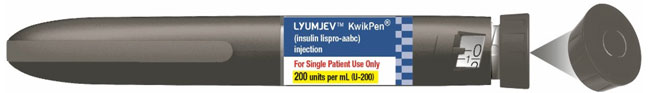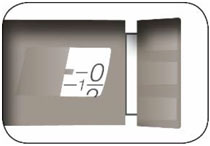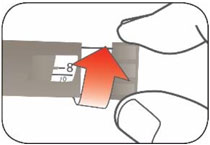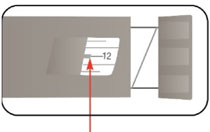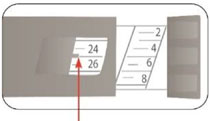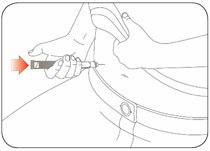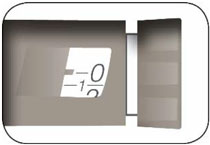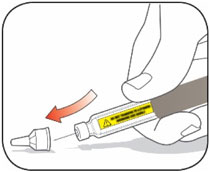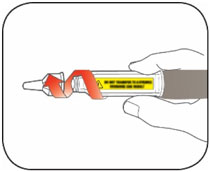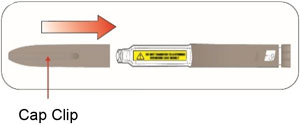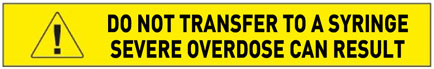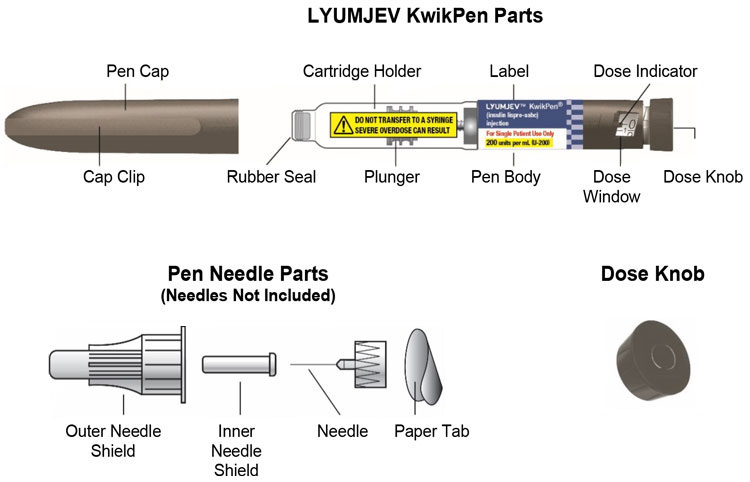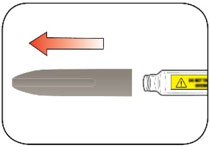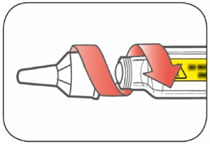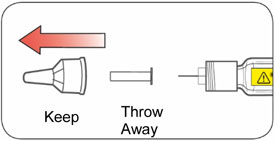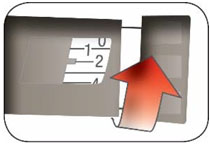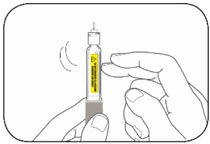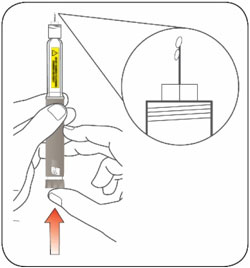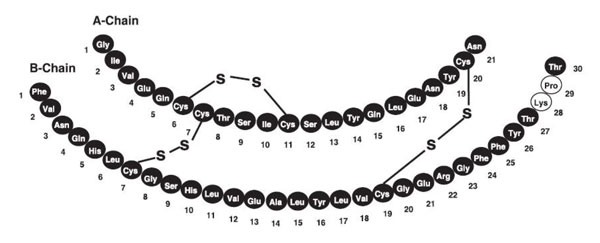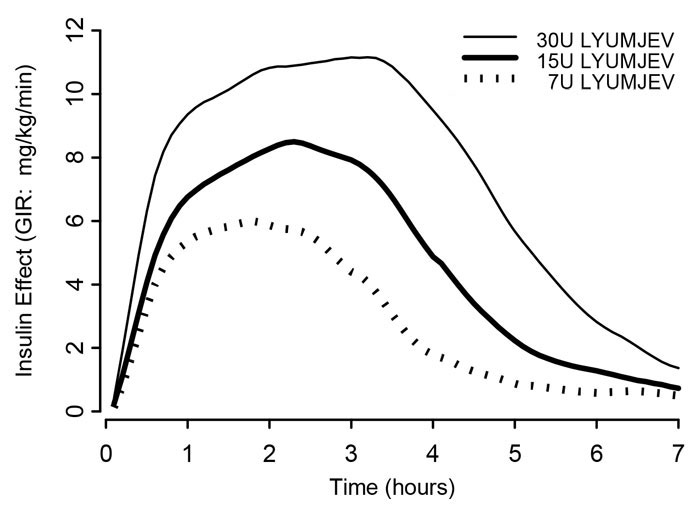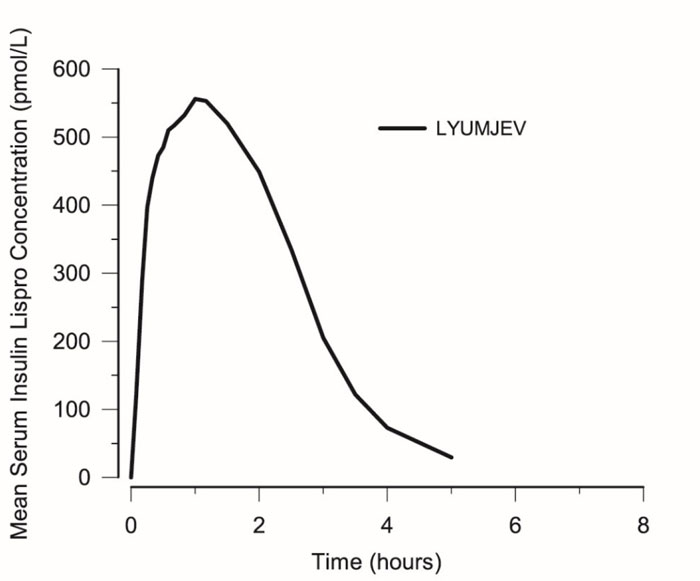 DRUG LABEL: LYUMJEV
NDC: 0002-7728 | Form: INJECTION, SOLUTION
Manufacturer: Eli Lilly and Company
Category: prescription | Type: HUMAN PRESCRIPTION DRUG LABEL
Date: 20251230

ACTIVE INGREDIENTS: Insulin lispro 100 [iU]/1 mL
INACTIVE INGREDIENTS: Treprostinil sodium 1.06 ug/1 mL; Trisodium citrate dihydrate 4.41 mg/1 mL; Zinc oxide; Magnesium chloride 1.02 mg/1 mL; Metacresol 3.15 mg/1 mL; Glycerin 12.1 mg/1 mL; Hydrochloric acid; Sodium hydroxide; Water

HIGHLIGHTS OF PRESCRIBING INFORMATION

These highlights do not include all the information needed to use LYUMJEV safely and effectively. See full prescribing information for LYUMJEV.
LYUMJEV (insulin lispro-aabc) injection, for subcutaneous or intravenous use
Initial U.S. Approval: 2020

RECENT MAJOR CHANGES

Indications and Usage (1) | 10/2022

1 INDICATIONS AND USAGE

LYUMJEV® is a rapid-acting human insulin analog indicated to improve glycemic control in adult and pediatric patients with diabetes mellitus. (1)

2 DOSAGE AND ADMINISTRATION

- See Full Prescribing Information for important administration instructions. (2.1, 2.2)
- Subcutaneous Injection (2.2):
  - Administer LYUMJEV U-100 or U-200 at the start of a meal or within 20 minutes after starting a meal subcutaneously into the abdomen, upper arm, thigh, or buttocks.
  - Rotate injection sites within the same region to reduce risk of lipodystrophy and localized cutaneous amyloidosis.
  - Should generally be used in regimens with an intermediate or long-acting insulin.
- Continuous subcutaneous infusion (Insulin Pump) (2.2):
  - Refer to the insulin infusion pump user manual to see if LYUMJEV can be used. Use in accordance with the insulin pump instructions for use.
  - Administer LYUMJEV U-100 by continuous subcutaneous infusion using an insulin pump in a region recommended in the instructions from the pump manufacturer. Rotate infusion sites within the same region to reduce the risk of lipodystrophy and localized cutaneous amyloidosis.
  - Do not administer LYUMJEV U-200 by continuous subcutaneous infusion.
- Intravenous Infusion (2.2):
  - Administer LYUMJEV U-100 intravenously only under medical supervision. DO NOT administer LYUMJEV U-200 by intravenous infusion.
  - Dilute LYUMJEV U-100 to a concentration of 1 unit/mL.
- Individualize and adjust the dosage of LYUMJEV based on the patient's metabolic needs, glucose monitoring results, and glycemic control goal. (2.3)
- Dose adjustments may be needed when switching from another insulin, with changes in physical activity, changes in concomitant medications, changes in meal patterns (i.e., amount and type of food, timing of food intake), changes in renal or hepatic function, or during acute illness. (2.3)

3 DOSAGE FORMS AND STRENGTHS

Injection: 100 units/mL (U-100) available as:

- 10 mL multiple-dose vial (3)
- 3 mL single-patient-use KwikPen® (3)
- 3 mL single-patient-use Junior KwikPen® (3)
- 3 mL single-patient-use Tempo Pen® (3)
- 3 mL single-patient-use cartridges (3)

Injection: 200 units/mL (U-200) available as:

- 3 mL single-patient-use KwikPen® (3)

4 CONTRAINDICATIONS

- During episodes of hypoglycemia. (4)
- Hypersensitivity to insulin lispro-aabc or any of the excipients in LYUMJEV. (4)

5 WARNINGS AND PRECAUTIONS

- Never share a LYUMJEV prefilled pen or cartridge between patients, even if the needle is changed. (5.1)
- Hyperglycemia or hypoglycemia with changes in insulin regimen: Make changes to a patient's insulin regimen (e.g., insulin strength, manufacturer, type, injection site or method of administration) under close medical supervision with increased frequency of glucose monitoring. (5.2)
- Hypoglycemia: May be life-threatening. Increase frequency of glucose monitoring with changes to: insulin dosage, co-administered glucose lowering medications, meal pattern, physical activity; and in patients with renal impairment or hepatic impairment or hypoglycemia unawareness. (5.3)
- Hypoglycemia due to medication errors: Accidental mix-ups between insulin products can occur. Instruct patients to check insulin labels before injection. Do not transfer LYUMJEV U-200 from the LYUMJEV KwikPen to a syringe as overdosage and severe hypoglycemia can result. (5.4)
- Hypokalemia: May be life-threatening. Monitor potassium levels in patients at risk for hypokalemia and treat if indicated. (5.5)
- Hypersensitivity reactions: Severe, life-threatening, generalized allergy, including anaphylaxis, can occur. Discontinue LYUMJEV, monitor, and treat if indicated. (5.6)
- Fluid retention and heart failure with concomitant use of thiazolidinediones (TZDs): Observe for signs and symptoms of heart failure; consider dosage reduction or discontinuation of TZD if heart failure occurs. (5.7)
- Hyperglycemia and ketoacidosis due to insulin pump device malfunction: Monitor glucose and administer LYUMJEV by subcutaneous injection if pump malfunction occurs. (5.8)

6 ADVERSE REACTIONS

Adverse reactions observed with LYUMJEV include hypoglycemia, injection/infusion site reactions, allergic reactions, rash, pruritus, lipodystrophy, and weight gain. (6.1)

To report SUSPECTED ADVERSE REACTIONS, contact Eli Lilly and Company at 1-800-LillyRx (1-800-545-5979) or FDA at 1-800-FDA-1088 or www.fda.gov/medwatch.

7 DRUG INTERACTIONS

- Drugs that Increase Hypoglycemia Risk or Increase or Decrease Blood Glucose Lowering Effect: Adjustment of dosage may be needed; closely monitor blood glucose. (7)
- Drugs that Blunt Hypoglycemia Signs and Symptoms (e.g., beta-blockers, clonidine, guanethidine, and reserpine): Increased frequency of glucose monitoring may be required. (7)

FULL PRESCRIBING INFORMATION

1 INDICATIONS AND USAGE

LYUMJEV® is indicated to improve glycemic control in adult and pediatric patients with diabetes mellitus.

2 DOSAGE AND ADMINISTRATION

2.1 Important Administration Instructions

- Always check insulin labels before administration [see Warnings and Precautions (5.4)].
- Inspect LYUMJEV visually before use. It should appear clear and colorless. Do not use LYUMJEV if particulate matter and discoloration is seen.
- Use LYUMJEV prefilled pens with caution in patients with visual impairment that may rely on audible clicks to dial their dose.
- Do not perform dose conversion when using any LYUMJEV U-100 or U-200 prefilled pens. The dose window of LYUMJEV prefilled pens shows the number of units of LYUMJEV to be delivered and no conversion is needed.
- Do not transfer LYUMJEV U-200 from the prefilled pen to a syringe for administration [see Warnings and Precautions (5.4)].
- Do not mix LYUMJEV with any other insulin products.
- Do not administer LYUMJEV U-200 using continuous subcutaneous infusion insulin pump.
- Do not administer LYUMJEV U-200 intravenously.

2.2 Route of Administration Instructions

Subcutaneous Injection for LYUMJEV U-100 or U-200

- Administer LYUMJEV at the start of a meal or within 20 minutes after starting a meal subcutaneously into the abdomen, upper arm, thigh, or buttocks.
- Rotate injection sites within the same region from one injection to the next to reduce the risk of lipodystrophy and localized cutaneous amyloidosis. Do not inject into areas of lipodystrophy or localized cutaneous amyloidosis [see Adverse Reactions (6.1, 6.2)].
- LYUMJEV given by subcutaneous injection should generally be used in regimens with intermediate or long-acting insulin.
- The LYUMJEV U-100 KwikPen, LYUMJEV U-100 Tempo Pen, and LYUMJEV U-200 KwikPen each dial in 1 unit increments and deliver a maximum dose of 60 units per injection.
- The LYUMJEV U-100 Junior KwikPen dials in 0.5 unit increments and delivers a maximum dose of 30 units per injection.

Continuous Subcutaneous Insulin Infusion (Insulin Pump) for LYUMJEV U-100 Only

- Do not administer LYUMJEV U-200 using an insulin pump.
- Refer to the continuous subcutaneous insulin infusion pump user manual to see if LYUMJEV can be used with the insulin pump. Use LYUMJEV in accordance with the insulin pump system's instructions for use.
- Administer LYUMJEV U-100 by continuous subcutaneous infusion in a region recommended in the instructions from the pump manufacturer. Rotate infusion sites within the same region to reduce the risk of lipodystrophy and localized cutaneous amyloidosis. Do not infuse into areas of lipodystrophy or localized cutaneous amyloidosis [see Warnings and Precautions (5.2) and Adverse Reactions (6.1)].
- Train patients using continuous subcutaneous insulin infusion (CSII) therapy to administer insulin by injection and have alternate insulin therapy available in case of insulin pump failure [see Warnings and Precautions (5.8)].
- Change LYUMJEV U-100 in the pump reservoir at least every 9 days or according to the pump user manual, whichever is shorter.
- Change the infusion sets and the infusion set insertion site according to the manufacturer's user manual.
- Do not dilute or mix LYUMJEV U-100 when administering by CSII.
- Do not expose LYUMJEV in the pump reservoir to temperatures greater than 98.6°F (37°C).

Intravenous Administration for LYUMJEV U-100 Only

- Do not administer LYUMJEV U-200 intravenously.
- Administer LYUMJEV U-100 intravenously only under medical supervision with close monitoring of glucose and potassium levels to avoid hypoglycemia and hypokalemia [see Warnings and Precautions (5.3, 5.5)].
- Dilute LYUMJEV U-100 to a concentration of 1 unit/mL using 0.9% Sodium Chloride Injection, USP or 5% Dextrose Injection, USP infusion solutions. Dilutions to concentrations below 1 unit/mL are not recommended.
- Diluted LYUMJEV may be stored for up to 4 days when refrigerated or up to 12 hours at room temperature [see HOW SUPPLIED/STORAGE AND HANDLING (16.2)].

2.3 General Dosage Instructions

- Individualize and adjust the dosage of LYUMJEV based on the patient's metabolic needs, glucose monitoring results, and glycemic control goal.
- If converting from another mealtime insulin to LYUMJEV, the change can be done on a unit-to-unit basis.
- Dosage adjustments may be needed when switching from another insulin, with changes in physical activity, changes in concomitant medications, changes in meal patterns (i.e., macronutrient content or timing of food intake), changes in renal or hepatic function or during acute illness to minimize the risk of hypoglycemia or hyperglycemia [see Warnings and Precautions (5.2, 5.3), Drug Interactions (7) and Use in Specific Populations (8.6, 8.7)].
- During changes to a patient's insulin regimen, increase the frequency of glucose monitoring [see Warnings and Precautions (5.2)].
- Instruct patients who forget a mealtime dose to monitor their glucose level to decide if an insulin dose is needed, and to resume their usual dosing schedule at the next meal.

3 DOSAGE FORMS AND STRENGTHS

Injection: 100 units/mL (U-100) clear and colorless solution available as:

- 10 mL multiple-dose vial
- 3 mL single-patient-use LYUMJEV KwikPen
- 3 mL single-patient-use LYUMJEV Junior KwikPen
- 3 mL single-patient-use LYUMJEV Tempo Pen
- 3 mL single-patient-use cartridges

Injection: 200 units/mL (U-200) clear and colorless solution available as:

- 3 mL single-patient-use LYUMJEV KwikPen

4 CONTRAINDICATIONS

LYUMJEV is contraindicated:

- during episodes of hypoglycemia.
- in patients with hypersensitivity to insulin lispro-aabc or any of the excipients in LYUMJEV.

5 WARNINGS AND PRECAUTIONS

5.1 Never Share a LYUMJEV Prefilled Pen, Cartridge, or Syringe Between Patients

LYUMJEV prefilled pens or cartridges should never be shared between patients, even if the needle is changed. Patients using LYUMJEV vials must never share needles or syringes with another person. Sharing poses a risk for transmission of blood-borne pathogens.

5.2 Hyperglycemia or Hypoglycemia with Changes in Insulin Regimen

Changes in an insulin regimen (e.g., insulin, insulin strength, manufacturer, type, injection site or method of administration) may affect glycemic control and predispose to hypoglycemia [see Warnings and Precautions (5.3)] or hyperglycemia. Repeated insulin injections into areas of lipodystrophy or localized cutaneous amyloidosis have been reported to result in hyperglycemia; and a sudden change in the injection site (to an unaffected area) has been reported to result in hypoglycemia [see Adverse Reactions (6.1)].

Make any changes to a patient's insulin regimen under close medical supervision with increased frequency of blood glucose monitoring. Advise patients who have repeatedly injected into areas of lipodystrophy or localized cutaneous amyloidosis to change the injection site to unaffected areas and closely monitor for hypoglycemia. For patients with type 2 diabetes, dosage adjustments of concomitant anti-diabetic products may be needed.

5.3 Hypoglycemia

Hypoglycemia is the most common adverse reaction associated with insulins, including LYUMJEV [see Adverse Reactions (6.1)]. Severe hypoglycemia can cause seizures, may lead to unconsciousness, may be life-threatening, or cause death. Hypoglycemia can impair concentration ability and reaction time; this may place an individual and others at risk in situations where these abilities are important (e.g., driving or operating other machinery). LYUMJEV, or any insulin, should not be used during episodes of hypoglycemia [see Contraindications (4)].

Hypoglycemia can happen suddenly and symptoms may differ in each individual and change over time in the same individual. Symptomatic awareness of hypoglycemia may be less pronounced in patients with longstanding diabetes, in patients with diabetic nerve disease, in patients using medications that block the sympathetic nervous system (e.g., beta-blockers) [see Drug Interactions (7)], or in patients who experience recurrent hypoglycemia.

Risk Factors for Hypoglycemia

The risk of hypoglycemia after an injection is related to the duration of action of the insulin and, in general, is highest when the glucose lowering effect of the insulin is maximal. The timing of hypoglycemia usually reflects the time-action profile of the administered insulin formulation. As with all insulins, the glucose lowering effect time course of LYUMJEV may vary in different individuals or at different times in the same individual and depends on many conditions, including the area of injection as well as the injection site blood supply and temperature [see Clinical Pharmacology (12.2)]. Other factors which may increase the risk of hypoglycemia include changes in meal pattern (e.g., macronutrient content or timing of meals), changes in level of physical activity, or changes to co-administered medication [see Drug Interactions (7)]. Patients with renal or hepatic impairment may be at higher risk of hypoglycemia [see Use in Specific Populations (8.6, 8.7)].

Risk Mitigation Strategies for Hypoglycemia

Patients and caregivers must be educated to recognize and manage hypoglycemia. Self-monitoring of glucose plays an essential role in the prevention and management of hypoglycemia. In patients at higher risk for hypoglycemia and patients who have reduced symptomatic awareness of hypoglycemia, increased frequency of glucose monitoring is recommended.

5.4 Hypoglycemia Due to Medication Errors

Accidental mix-ups between insulin products have been reported. To avoid medication errors between LYUMJEV and other insulins, instruct patients to always check the insulin label before each injection.

Do not transfer LYUMJEV U-200 from the LYUMJEV KwikPen to a syringe. The markings on the insulin syringe will not measure the dose correctly and can result in overdosage and severe hypoglycemia [see Dosage and Administration (2.1) and Warnings and Precautions (5.3)].

5.5 Hypokalemia

All insulins, including LYUMJEV, cause a shift in potassium from the extracellular to intracellular space, possibly leading to hypokalemia. Untreated hypokalemia may cause respiratory paralysis, ventricular arrhythmia, and death. Monitor potassium levels in patients at risk for hypokalemia if indicated (e.g., patients using potassium-lowering medications, patients taking medications sensitive to serum potassium concentrations).

5.6 Hypersensitivity Reactions

Severe, life-threatening, generalized allergy, including anaphylaxis, can occur with insulins, including LYUMJEV [see Adverse Reactions (6.1)]. If hypersensitivity reactions occur, discontinue LYUMJEV; treat per standard of care and monitor until symptoms and signs resolve. LYUMJEV is contraindicated in patients who have had hypersensitivity reactions to insulin lispro-aabc or any of its excipients [see Contraindications (4)].

5.7 Fluid Retention and Heart Failure with Concomitant Use of PPAR-Gamma Agonists

Thiazolidinediones (TZDs), which are peroxisome proliferator-activated receptor (PPAR)-gamma agonists, can cause dose-related fluid retention, particularly when used in combination with insulin. Fluid retention may lead to or exacerbate heart failure. Patients treated with insulin, including LYUMJEV, and a PPAR-gamma agonist should be observed for signs and symptoms of heart failure. If heart failure develops, it should be managed according to current standards of care, and discontinuation or dose reduction of the PPAR-gamma agonist must be considered.

5.8 Hyperglycemia and Ketoacidosis Due to Insulin Pump Device Malfunction

Pump or infusion set malfunctions can lead to a rapid onset of hyperglycemia and ketoacidosis. Prompt identification and correction of the cause of hyperglycemia or ketosis is necessary. Interim therapy with subcutaneous injection of LYUMJEV may be required. Patients using continuous subcutaneous insulin infusion pump therapy must be trained to administer insulin by injection and have alternate insulin therapy available in case of pump failure [see Dosage and Administration (2.2), How Supplied/Storage and Handling (16.2), and Patient Counseling Information (17)].

6 ADVERSE REACTIONS

The following adverse reactions are also discussed elsewhere:

- Hypoglycemia [see Warnings and Precautions (5.3)].
- Hypoglycemia Due to Medication Errors [see Warnings and Precautions (5.4)]
- Hypokalemia [see Warnings and Precautions (5.5)].
- Hypersensitivity Reactions [see Warnings and Precautions (5.6)].

6.1 Clinical Trials Experience

Because clinical trials are conducted under widely varying conditions, adverse reaction rates observed in the clinical trials of a drug cannot be directly compared to rates in the clinical trials of another drug, and may not reflect the rates actually observed in clinical practice.

Adverse Reaction Database – Adult Patients with Type 1 and Type 2 Diabetes

The data in Table 1 reflect the exposure of 780 adult patients with type 1 diabetes to LYUMJEV with a mean exposure duration of 26 weeks [see Clinical Studies (14.2)]. The mean age was 44 years, the mean duration of diabetes was 19 years, 55% were male, 77% were White, 2% were Black or African American, and 9% were Hispanic. The mean BMI was 26.6 kg/m^2 and the mean HbA1c at baseline was 7.3%.

The data in Table 2 reflect the exposure of 336 adult patients with type 2 diabetes to LYUMJEV with a mean exposure duration of 26 weeks [see Clinical Studies (14.3)]. The mean age was 60 years, the mean duration of diabetes was 16 years, 55% were male, 69% were White, 4% were Black or African American, and 24% were Hispanic. The mean BMI was 32.1 kg/m^2 and the mean HbA1c at baseline was 7.3%.

The data in Table 3 reflect the exposure of 215 adult patients with type 1 diabetes to LYUMJEV via CSII administration with a mean exposure duration of 16 weeks [see Clinical Studies (14.4)]. The mean age was 48 years, the mean duration of diabetes was 26 years, 44% were male, 94% were White, 3% were Black or African American, and 8% were Hispanic. The mean BMI was 27.0 kg/m^2 and the mean HbA1c at baseline was 7.6%.

Common adverse reactions, excluding hypoglycemia, were defined as events that occurred in ≥5% and at the same rate or greater for LYUMJEV-treated patients than HUMALOG-treated patients.

Table 1. Adverse Reactions That Occurred in ≥5% of LYUMJEV-Treated Adult Patients with Type 1 Diabetes
 | Mealtime LYUMJEV + basal insulin (N=451) % | Postmeal LYUMJEV + basal insulin (N=329) %
Nasopharyngitis | 14.2 | 14.6

Table 2. Adverse Reactions That Occurred in ≥5% of LYUMJEV-Treated Adult Patients with Type 2 Diabetes
 | Mealtime LYUMJEV + basal insulin (N=336) %
Nasopharyngitis | 12.5
Upper Respiratory Tract Infection | 7.4

Table 3. Adverse Reactions That Occurred in ≥5% of LYUMJEV-Treated Adult Patients with Type 1 Diabetes Using Continuous Subcutaneous Insulin Infusion
 | CSII LYUMJEV administration (N=215) %
Infusion site reaction | 19.1
Infusion site pain | 15.8
Nasopharyngitis | 6.0

Adverse Reaction Database – Pediatric Patients with Type 1 Diabetes

The data in Table 4 reflect the exposure of 418 pediatric patients with type 1 diabetes to LYUMJEV with a mean exposure duration of 26 weeks [see Clinical Studies (14.5)]. The mean age was 12 years; 50% were male, 91% were White, 1% were Black or African American; and 24% of the US subpopulation in this trial were Hispanic. The mean BMI was 20.5 kg/m^2, the mean duration of diabetes was 5 years, and the mean HbA1c at baseline was 7.8%. Common adverse reactions, excluding hypoglycemia, were defined as events that occurred in ≥5% and at the same rate or greater for LYUMJEV-treated patients than HUMALOG-treated patients.

Table 4. Adverse Reactions That Occurred in ≥5% of LYUMJEV-Treated Pediatric Patients with Type 1 Diabetes
 | Mealtime LYUMJEV + basal insulin (N=280) % | Postmeal LYUMJEV + basal insulin (N=138) %
Nasopharyngitis | 8.2 | 5.1
Upper Respiratory Tract Infection | 5.4 | 1.4

Hypoglycemia

Hypoglycemia is the most commonly observed adverse reaction in patients using insulin, including LYUMJEV. The rates of reported hypoglycemia depend on the definition of hypoglycemia used, diabetes type, insulin dose, intensity of glucose control, background therapies, and other intrinsic and extrinsic patient factors. For these reasons, comparing rates of hypoglycemia in clinical trials for LYUMJEV with the incidence of hypoglycemia for other products may be misleading and also may not be representative of hypoglycemia rates that occur in clinical practice.

Incidence rates for severe hypoglycemia in adults with type 1 and type 2 diabetes mellitus and pediatric patients with type 1 diabetes mellitus treated with LYUMJEV in clinical trials are shown in Table 5 [see Clinical Studies (14)].

Table 5. Proportion of Patients with Type 1 Diabetes and Type 2 Diabetes Who Experienced at Least One Episode of Severe Hypoglycemia in Adult and Pediatric Clinical Trials
 | PRONTO-T1D (Adult Type 1) |  | PRONTO-T2D (Adult Type 2) | PRONTO-Pump-2 (Adult Type 1 CSII) | PRONTO-Peds (Pediatric Type 1)
 | Mealtime LYUMJEV + basal insulin (N=451) % | Postmeal LYUMJEV + basal insulin (N=329) % | Mealtime LYUMJEV + basal insulin (N=336) % | LYUMJEV (N=215) % | Mealtime LYUMJEV + basal insulin (N=280) % | Postmeal LYUMJEV + basal insulin (N=298) %
Severe hypoglycemiaa | 5.5 | 4.6 | 0.9 | 1.4 | 1.1 | 0
a Severe hypoglycemia: an episode requiring assistance of another person to actively administer carbohydrate, glucagon, or other resuscitative actions

Allergic Reactions

Severe, life-threatening, generalized allergy, including anaphylaxis, generalized skin reactions, angioedema, bronchospasm, hypotension, and shock may occur with any insulin, including LYUMJEV, and may be life threatening. Generalized hypersensitivity reactions such as skin rashes and hypersensitivity were reported in adult patients treated with LYUMJEV: eczema (0.4%), rash (0.4%), dermatitis (0.3%), hypersensitivity (0.2%), and pruritus (0.2%).

Generalized hypersensitivity reactions reported in more than 1 pediatric patient treated with LYUMJEV included: rhinitis (0.7%), dermatitis (0.7%), rash (0.5%), and hypersensitivity (0.5%).

Lipodystrophy

Administration of insulin, including LYUMJEV, has resulted in lipohypertrophy (enlargement or thickening of tissue) and lipoatrophy (depression in the skin). Lipodystrophy was reported in 0.2% of adult and pediatric patients treated with LYUMJEV [see Dosage and Administration (2.2)].

Injection/Infusion Site Reactions

Injection or infusion site reactions can occur with insulin therapy. With LYUMJEV, adult and pediatric patients have experienced rash, redness, inflammation, pain, bruising, or itching at the site of LYUMJEV injection or infusion. LYUMJEV contains treprostinil sodium and sodium citrate dihydrate as inactive ingredients [see Description (11)] which have been associated with infusion and injection site reactions with other non-insulin products.

Subcutaneous Injection Site-Related Reactions:

In studies PRONTO-T1D and PRONTO-T2D, injection site-related reactions occurred in 2.7% of adult patients treated with LYUMJEV (mild in 2.2% and moderate in 0.5%). with <0.1% of patients discontinuing from treatment due to injection site-related reactions.

In Study PRONTO-Peds, injection site-related reactions occurred in 6.2% of pediatric patients treated with LYUMJEV (mild in 5.7% and moderate in 0.5%), with <0.5% of patients discontinuing from treatment due to injection site-related reactions.

Continuous Subcutaneous Insulin Infusion (CSII) Site-Related Reactions:

In Study PRONTO-Pump-2, infusion site-related reactions were reported in 37.7% of adult patients treated with LYUMJEV (mild in 27.9%, moderate in 7.9%, and severe in 1.9%), with 3.3% of patients discontinuing from treatment due to infusion site-related reactions. See Table 4.

Weight Gain

Weight gain can occur with insulin therapy, including LYUMJEV, and has been attributed to the anabolic effects of insulin and the decrease in glucosuria. Adult patients with type 1 diabetes treated with LYUMJEV gained an average of 0.6 kg and patients with type 2 diabetes treated with LYUMJEV gained an average of 1.5 kg.

Peripheral Edema

Insulin, including LYUMJEV, may cause sodium retention and edema, particularly if previous poor metabolic control is improved by intensified insulin therapy. Peripheral edema occurred in 0.2% of adult patients treated with LYUMJEV.

6.2 Postmarketing Experience

The following additional adverse reactions have been identified during post-approval use of insulin lispro. Because these reactions are reported voluntarily from a population of uncertain size, it is not always possible to reliably estimate their frequency or establish a causal relationship to drug exposure.

Localized cutaneous amyloidosis at the injection site has occurred with insulin use. Hyperglycemia has been reported with repeated insulin injections into areas of localized cutaneous amyloidosis; hypoglycemia has been reported with a sudden change to an unaffected injection site.

7 DRUG INTERACTIONS

Table 6 includes clinically significant drug interactions with LYUMJEV.

Table 6. Clinically Significant Drug Interactions with LYUMJEV
Drugs That May Increase the Risk of Hypoglycemia
Drugs: | Antidiabetic agents, ACE inhibitors, angiotensin II receptor blocking agents, disopyramide, fibrates, fluoxetine, monoamine oxidase inhibitors, pentoxifylline, pramlintide, salicylates, somatostatin analogs (e.g., octreotide), and sulfonamide antibiotics.
Intervention: | Dose reductions and increased frequency of glucose monitoring may be required when LYUMJEV is co-administered with these drugs.
Drugs That May Decrease the Blood Glucose Lowering Effect of LYUMJEV
Drugs: | Atypical antipsychotics (e.g., olanzapine and clozapine), corticosteroids, danazol, diuretics, estrogens, glucagon, isoniazid, niacin, oral contraceptives, phenothiazines, progestogens (e.g., in oral contraceptives), protease inhibitors, somatropin, sympathomimetic agents (e.g., albuterol, epinephrine, terbutaline), and thyroid hormones.
Intervention: | Dose increases and increased frequency of glucose monitoring may be required when LYUMJEV is co-administered with these drugs.
Drugs That May Increase or Decrease the Blood Glucose Lowering Effect of LYUMJEV
Drugs: | Alcohol, beta-blockers, clonidine, and lithium salts. Pentamidine may cause hypoglycemia, which may sometimes be followed by hyperglycemia.
Intervention: | Dose adjustment and increased frequency of glucose monitoring may be required when LYUMJEV is co-administered with these drugs.
Drugs That May Blunt Signs and Symptoms of Hypoglycemia
Drugs: | Beta-blockers, clonidine, guanethidine, and reserpine.
Intervention: | Increased frequency of glucose monitoring may be required when LYUMJEV is co-administered with these drugs.

8 USE IN SPECIFIC POPULATIONS

8.1 Pregnancy

Risk Summary

Published studies with insulin lispro used during pregnancy have not reported an association between insulin lispro and the induction of major birth defects, miscarriage, or adverse maternal or fetal outcomes (see Data). There are risks to the mother and fetus associated with poorly controlled diabetes in pregnancy (see Clinical Considerations). Pregnant rats and rabbits were exposed to insulin lispro in animal reproduction studies during organogenesis. No adverse effects on embryo/fetal viability or morphology were observed in offspring of rats exposed to insulin lispro at a dose approximately 3 times the human subcutaneous dose of 1 unit insulin lispro/kg/day. No adverse effects on embryo/fetal development were observed in offspring of rabbits exposed to insulin lispro at doses up to approximately 0.2 times the human subcutaneous dose of 1 unit/kg/day (see Data).

The estimated background risk of major birth defects is 6% to 10% in women with pre-gestational diabetes with a HbA1c>7 and has been reported to be as high as 20% to 25% in women with a HbA1c>10. The estimated background risk of miscarriage for the indicated population is unknown. In the U.S. general population, the estimated background risk of major birth defects and miscarriage in clinically recognized pregnancies is 2% to 4% and 15% to 20%, respectively.

Clinical Considerations

Disease-associated Maternal and/or Embryo-Fetal Risk

Poorly controlled diabetes in pregnancy increases the maternal risk for diabetic ketoacidosis, pre-eclampsia, spontaneous abortions, preterm delivery, and delivery complications. Poorly controlled diabetes increases the fetal risk for major birth defects, stillbirth, and macrosomia related morbidity.

Data

Human Data

Published data from retrospective studies and meta-analyses do not report an association with insulin lispro and major birth defects, or adverse maternal or fetal outcomes when insulin lispro is used during pregnancy. However, these studies cannot definitely establish or exclude the absence of any risk because of methodological limitations including small sample size, selection bias, confounding by unmeasured factors, and some lacking comparator groups.

Animal Data

Animal reproduction studies have not been performed with LYUMJEV. However, subcutaneous reproduction and teratology studies have been conducted with insulin lispro. In a combined fertility and embryo-fetal development study, female rats were given subcutaneous insulin lispro injections of 1, 5, and 20 units/kg/day (0.2, 0.8, and 3 times the human subcutaneous dose of 1 unit insulin lispro/kg/day, based on units/body surface area, respectively) from 2 weeks prior to cohabitation through Gestation Day 19. There were no adverse effects on female fertility, implantation, or fetal viability and morphology. However, fetal growth retardation was produced at the 20 units/kg/day-dose as indicated by decreased fetal weight and an increased incidence of fetal runts/litter.

In an embryo-fetal development study in pregnant rabbits, insulin lispro doses of 0.1, 0.25, and 0.75 unit/kg/day (0.03, 0.08, and 0.2 times the human subcutaneous dose of 1 unit insulin lispro/kg/day, based on units/body surface area, respectively) were injected subcutaneously on Gestation Days 7 through 19. There were no adverse effects on fetal viability, weight, and morphology at any dose.

8.2 Lactation

Risk Summary

Available data from published literature suggests that exogenous human insulin products, including insulin lispro, are transferred into human milk. There are no adverse reactions reported in breastfed infants in the literature. There are no data on the effects of exogenous human insulin products, including insulin lispro, on milk production. The developmental and health benefits of breastfeeding should be considered along with the mother's clinical need for insulin, any potential adverse effects on the breastfed child from LYUMJEV or from the underlying maternal condition.

8.4 Pediatric Use

The safety and effectiveness of LYUMJEV to improve glycemic control in pediatric patients with diabetes mellitus have been established. Use of LYUMJEV for this indication is supported by evidence from an adequate and well-controlled study in 716 pediatric patients with type 1 diabetes mellitus aged 1 year and older, and from studies in adult and pediatric patients with diabetes mellitus [see Clinical Pharmacology (12.3) and Clinical Studies (14.5)].

LYUMJEV-treated pediatric patients reported a higher incidence of subcutaneous injection site-related reactions compared to LYUMJEV-treated adults [see Adverse Reactions (6.1)]. It is expected that LYUMJEV-treated pediatric patients who receive continuous subcutaneous insulin infusion (CSII) are more likely to have infusion site-related adverse reactions than those who receive subcutaneous injections [see Adverse Reactions (6.1)]. Monitor injection and infusion sites closely when initiating therapy with LYUMJEV in pediatric patients. If persistent injection or infusion site reactions occur, discontinue LYUMJEV and initiate therapy with an alternative insulin.

8.5 Geriatric Use

Of the total number of LYUMJEV-treated patients in clinical studies for type 1 or type 2 diabetes (PRONTO-T1D and PRONTO-T2D, respectively), 17% (187/1,116) were 65 years of age and older, while 2% (18/1,116) were 75 years of age and older [see Clinical Studies (14.2, 14.3)].

No overall differences in safety or effectiveness of LYUMJEV have been observed between patients 65 years of age and older and younger adult patients.

8.6 Renal Impairment

Patients with renal impairment may be at increased risk of hypoglycemia and may require more frequent LYUMJEV dose adjustment and more frequent glucose monitoring [see Warnings and Precautions (5.3) and Clinical Pharmacology (12.3)].

8.7 Hepatic Impairment

Patients with hepatic impairment may be at increased risk of hypoglycemia and may require more frequent LYUMJEV dose adjustment and more frequent glucose monitoring [see Warnings and Precautions (5.3) and Clinical Pharmacology (12.3)].

10 OVERDOSAGE

Excess insulin administration may cause hypoglycemia and hypokalemia [see Warnings and Precautions (5.3, 5.5)]. Mild episodes of hypoglycemia usually can be treated with oral glucose. Adjustments in drug dosage, meal patterns, or exercise, may be needed. More severe episodes with coma, seizure, or neurologic impairment may be treated with glucagon or concentrated intravenous glucose. Sustained carbohydrate intake and observation may be necessary because hypoglycemia may recur after apparent clinical recovery. Hypokalemia must be corrected appropriately.

11 DESCRIPTION

Insulin lispro-aabc is a rapid-acting human insulin analog used to lower blood glucose. Insulin lispro-aabc is produced by recombinant DNA technology utilizing a non-pathogenic laboratory strain of Escherichia coli. Insulin lispro-aabc differs from human insulin in that the amino acid proline at position B28 is replaced by lysine and the lysine in position B29 is replaced by proline. Chemically, it is Lys(B28), Pro(B29) human insulin analog and has the empirical formula C257H383N65O77S6 and a molecular weight of 5808 daltons, both identical to that of human insulin.

Insulin lispro-aabc has the following primary structure:

LYUMJEV (insulin lispro-aabc) injection is a sterile, aqueous, clear, and colorless solution for subcutaneous or intravenous administration. Each mL of LYUMJEV U-100 contains 100 units of insulin lispro-aabc and the inactive ingredients: glycerol (12.1 mg), magnesium chloride hexahydrate (1.02 mg), metacresol (3.15 mg), sodium citrate dihydrate (4.41 mg), treprostinil sodium (1.06 mcg), zinc oxide (content adjusted to provide 39 mcg zinc ion), and Water for Injection, USP.

Each mL of LYUMJEV U-200 contains 200 units of insulin lispro-aabc and the inactive ingredients: glycerol (12.1 mg), magnesium chloride hexahydrate (1.02 mg), metacresol (3.15 mg), sodium citrate dihydrate (4.41 mg), treprostinil sodium (1.06 mcg), zinc oxide (content adjusted to provide 52 mcg zinc ion), and Water for Injection, USP.

Hydrochloric acid and/or sodium hydroxide may be added to adjust the pH. LYUMJEV has a pH of 7.0 to 7.8.

12 CLINICAL PHARMACOLOGY

12.1 Mechanism of Action

The primary activity of LYUMJEV is the regulation of glucose metabolism. Insulins, including insulin lispro-aabc, exert their specific action through binding to insulin receptors. Receptor-bound insulin lowers glucose by stimulating peripheral glucose uptake by skeletal muscle and fat, and by inhibiting hepatic glucose production. Insulins inhibit lipolysis and proteolysis, and enhance protein synthesis.

12.2 Pharmacodynamics

The time course of insulin action (i.e., glucose lowering) may vary considerably in different individuals or within the same individual. The average pharmacodynamic profile [i.e., glucose lowering effect measured as glucose infusion rate (GIR) in a euglycemic clamp study] for subcutaneous administration of 7, 15, and 30 units of LYUMJEV in 42 healthy subjects is shown in Figure 1 and key characteristics of the timing of the effect are described in Table 7 below.

Figure 1. Mean Insulin Effect Over Time After Subcutaneous Administration of 7, 15, and 30 units of LYUMJEV in Healthy Subjects.

Table 7. Timing of Insulin Effect (i.e., Mean Pharmacodynamic Effect) After Subcutaneous Administration of 7, 15, and 30 Units of LYUMJEV in Healthy Subjects (N=42) and Corresponding to the Data Shown in Figure 1
Parameter for Insulin Effect | LYUMJEV 7 units | LYUMJEV 15 units | LYUMJEV 30 units
Time to first measurable effect | ~17 minutes | ~17 minutes | ~15 minutes
Time to peak effect | ~120 minutes | ~138 minutes | ~174 minutes
Time for effect to return to baseline | ~4.6 hours | ~6.2 hours | ~7.3 hours

On average, the pharmacodynamic effects of LYUMJEV, measured as area under the glucose infusion rate-time curve (AUCGIR), was 1080 mg/kg, 1860 mg/kg, and 3030 mg/kg following administration of 7, 15, and 30 units of LYUMJEV in healthy subjects.

Similar pharmacodynamic profiles were observed in separate studies conducted in 40 patients with type 1 diabetes and 38 patients with type 2 diabetes given LYUMJEV subcutaneously as a single 15 unit dose.

The onset and total glucose lowering were similar when LYUMJEV was administered in the abdomen, deltoid, or thigh. The day-to-day variability [percent coefficient of variation (CV%)] within subjects in the glucose-lowering-effect of LYUMJEV was 24% for the early glucose lowering (AUCGIR, 0-1h), 27% for the total glucose lowering (AUCGIR, 0-10h), and 19% for maximum glucose lowering effect (GIRmax).

Postprandial Glucose Lowering

When given at the start of a meal or 20 minutes after the start of the meal, LYUMJEV reduced postprandial glucose during a standardized test meal over the complete 5-hour period [change from premeal AUC(0-5h)] in patients with type 1 or type 2 diabetes.

The maximum and total glucose lowering were comparable for a single 15 unit dose of LYUMJEV 200 units/mL or LYUMJEV 100 units/mL when administered subcutaneously to healthy subjects. The insulin time action profile with LYUMJEV 200 units/mL was the same as observed with LYUMJEV 100 units/mL.

12.3 Pharmacokinetics

Absorption

Absorption of insulin lispro-aabc was evaluated in healthy subjects (see Figure 2) and patients with diabetes following subcutaneous injection of LYUMJEV.

- Insulin lispro-aabc appeared in circulation approximately 1 minute after injection of LYUMJEV.
- Time to 50% maximum insulin lispro-aabc concentration was 13 minutes.
- Time to maximum insulin lispro-aabc concentration was achieved at 57 minutes.

In healthy subjects, the day-to-day variability [CV%] within subjects of LYUMJEV was 10% for total exposure (AUC, 0-10h) and 16% for maximum insulin lispro-aabc concentration (Cmax).

Figure 2. Mean Serum Insulin Lispro-aabc After Subcutaneous Injection of LYUMJEV (15 unit dose) in Healthy Subjects

The absolute bioavailability of insulin lispro-aabc after subcutaneous administration of LYUMJEV in the abdomen, deltoid, and thigh was approximately 65%. The rate of absorption of insulin lispro-aabc is maintained regardless of injection site. Maximum concentration and time to maximum concentration were comparable for the abdomen and upper arm regions; time to maximum concentration was longer and maximum concentration was lower for the thigh.

Total insulin lispro-aabc exposure and maximum insulin lispro-aabc concentration increased proportionally with increasing subcutaneous doses of LYUMJEV within the therapeutic dose range.

The results of a study in healthy subjects demonstrated that LYUMJEV 200 units/mL is bioequivalent to LYUMJEV 100 units/mL following administration of a single 15 unit dose for the area under the serum insulin lispro-aabc concentration-time curve from time zero to infinity and maximum insulin lispro-aabc concentration. The rate of insulin lispro-aabc absorption after administration of LYUMJEV 200 units/mL was similar as observed with LYUMJEV 100 units/mL.

Distribution

Following a 15 unit intravenous bolus injection of LYUMJEV in healthy subjects, the geometric mean (CV%) volume of distribution of insulin lispro-aabc (Vd) was 34 L (30%).

Elimination

Following a 15 unit intravenous bolus injection of LYUMJEV in healthy subjects, the geometric mean (CV%) clearance of insulin lispro-aabc was 32 L/hour (22%) and the median half-life of insulin lispro-aabc was 44 minutes.

Specific Populations

Age, biological sex, and race did not affect the pharmacokinetics and pharmacodynamics of LYUMJEV.

Patients with Renal and Hepatic Impairment

Renal and hepatic impairment is not known to impact the pharmacokinetics of insulin lispro-aabc. Insulin requirements may be reduced in the presence of renal or hepatic impairment.

12.6 Immunogenicity

The observed incidence of anti-drug antibodies is highly dependent on the sensitivity and specificity of the assay. Differences in assay methods preclude meaningful comparisons of the incidence of anti-drug antibodies in the studies described below with the incidence of anti-drug antibodies in other studies, including those of insulin lispro-aabc or of other insulin lispro products.

In a 26-week trial in adult patients with type 1 diabetes (Study PRONTO-T1D) [see Clinical Studies (14.2)], 49% of LYUMJEV-treated patients were anti-drug (insulin lispro-aabc) antibody (ADA)-positive at baseline, 91% of whom had cross-reactive antibodies with native insulin. During this 26-week period in this trial, 33% of LYUMJEV-treated patients had treatment-emergent ADA post-baseline (i.e., either new ADA or a 57% increase in assay signal over baseline), 75% of whom had cross-reactive antibodies with native insulin.

In a 26-week trial in adult patients with type 2 diabetes (Study PROTO-T2D) [see Clinical Studies (14.3)], 35% of LYUMJEV-treated patients were ADA-positive at baseline, 81% of whom had cross-reactive antibodies with native insulin. During this 26-week period in this trial, 31% of LYUMJEV-treated patients had treatment-emergent ADA post-baseline (i.e., either new ADA or a 57% increase in assay signal over baseline), 68% of whom had cross-reactive antibodies with native insulin.

In a 26-week trial in pediatric patients with type 1 diabetes (Study-PRONTO-PEDS) [see Clinical Studies (14.5)], 73% of LYUMJEV-treated patients were ADA-positive at baseline. Of these ADA-positive patients, 97% had cross-reactive antibodies with native insulin. During this 26-week period in this trial, 31% of LYUMJEV-treated patients had treatment-emergent ADA post-baseline (i.e., either new ADA or a 57% increase in assay signal over baseline). Of these treatment-emergent ADA-positive patients, 84% had cross-reactive antibodies with native insulin.

In these clinical trials, there were no identified clinically significant effects of ADA on safety or effectiveness (measured by HbA1c) of LYUMJEV over the treatment duration of 26-weeks.

13 NONCLINICAL TOXICOLOGY

13.1 Carcinogenesis, Mutagenesis, Impairment of Fertility

In Fischer 344 rats, a 12-month repeat-dose toxicity study was conducted with insulin lispro at subcutaneous doses of 20 and 200 units/kg/day (approximately 3 and 32 times the human subcutaneous dose of 1 unit/kg/day, based on units/body surface area). Insulin lispro did not produce important target organ toxicity including mammary tumors at any dose.

Insulin lispro was not mutagenic in the following genetic toxicity assays: bacterial mutation, unscheduled DNA synthesis, mouse lymphoma, chromosomal aberration, and micronucleus assays.

Male fertility was not compromised when male rats given subcutaneous insulin lispro injections of 5 and 20 units/kg/day (0.8 and 3 times the human subcutaneous dose of 1 unit/kg/day, based on units/body surface area) for 6 months were mated with untreated female rats. In a combined fertility, perinatal, and postnatal study in male and female rats given 1, 5, and 20 units/kg/day subcutaneously (0.2, 0.8, and 3 times the human subcutaneous dose of 1 unit/kg/day, based on units/body surface area), mating and fertility were not adversely affected in either gender at any dose.

14 CLINICAL STUDIES

14.1 Overview of Clinical Studies

The effectiveness of LYUMJEV was evaluated in:

- Two randomized, active controlled trials of 26 weeks in adults with type 1 diabetes (N=780) or type 2 diabetes (N=336) (PRONTO-T1D and PRONTO-T2D, respectively) [see Clinical Studies (14.2, 14.3)].
- A randomized, active controlled 16-week trial in adults with type 1 diabetes using continuous subcutaneous insulin infusion (N=432) (PRONTO-Pump-2) [see Clinical Studies (14.4)].
- A randomized, active controlled 26-week trial in pediatric patients with type 1 diabetes (N=716) (PRONTO-Peds) [see Clinical Studies (14.5)].

14.2 Adults with Type 1 Diabetes

PRONTO-T1D (NCT03214367) was a 26 week, randomized (4:4:3), active controlled, treat-to-target, multinational trial that evaluated the efficacy of LYUMJEV in 1222 adult patients with type 1 diabetes. Patients were randomized to either blinded mealtime LYUMJEV (N=451), blinded mealtime HUMALOG (N=442), or open-label postmeal LYUMJEV (N=329), all in combination with either insulin glargine or insulin degludec. Mealtime LYUMJEV or HUMALOG was injected 0 to 2 minutes before the meal and postmeal LYUMJEV was injected 20 minutes after the start of the meal.

Patients had a mean age of 44 years; mean duration of diabetes of 19 years; 56% were male; race: 77% White, 19% Asian, and 2% Black or African American. Eight percent of the randomized patients were Hispanic. The mean BMI was 26.6 kg/m^2.

At week 26, treatment with mealtime LYUMJEV provided a mean reduction in HbA1c that met the pre-specified non-inferiority margin (0.4%) (see Table 8). In addition, postmeal LYUMJEV met the prespecified non-inferiority margin (0.4%) compared to mealtime HUMALOG. Insulin doses were similar in all treatment groups at baseline and at 26 weeks.

Table 8. Results from Study PRONTO-T1D: 26 Week Trial of Mealtime LYUMJEV and Postmeal LYUMJEV compared with Mealtime HUMALOG, all in Combination with Basal Insulin in Adults with Type 1 Diabetes
 | Mealtime LYUMJEV + basal insulin | Mealtime HUMALOG + basal insulin | Postmeal LYUMJEV + basal insulin
Number of randomized subjects (N) | 451 | 442 | 329
HbA 1c (%) (mean) a
Baseline | 7.3 | 7.3 | 7.4
Adjusted mean change from baselineb | -0.12 | -0.04 | 0.1
Estimated treatment difference versus HUMALOG [95% CI] | -0.08 [-0.16, 0.00]c |  | 0.14 [0.05, 0.22]
a Analysis population: all randomized subjects regardless of adherence to treatment or availability of post-baseline assessment. Missing data at Week 26 were imputed by return to baseline approach. At week 26, primary efficacy assessment was missing for 3.8%, 4.8%, and 5.2% of subjects, for mealtime LYUMJEV, mealtime HUMALOG, and postmeal LYUMJEV, respectively.
b Least-squares (LS) mean from ANCOVA adjusted for baseline value and other stratification factors.
c Tested for non-inferiority.

14.3 Adults with Type 2 Diabetes

PRONTO-T2D (NCT03214380) was a 26-week, randomized (1:1), active controlled, treat-to-target, multinational trial that evaluated the efficacy of LYUMJEV in 673 adult patients with type 2 diabetes who at study entry were on multiple daily injections with either basal insulin and at least one prandial insulin injection or premixed insulin with at least two injections daily. Patients may also have been treated with up to three oral anti-diabetic medications (OAMs) in addition to insulin. Patients were allowed to continue on metformin and/or a SGLT2 inhibitor and were randomized to either mealtime LYUMJEV (N=336) or to mealtime HUMALOG (N=337), both in combination with insulin glargine or insulin degludec in a basal-bolus regimen. Mealtime LYUMJEV or mealtime HUMALOG was injected 0-2 minutes before the meal.

Patients had a mean age of 61 years; mean duration of diabetes of 17 years; 53% were male; race: 69% White, 24% Asian, and 5% Black or African American. Twenty-three percent of the randomized patients were Hispanic. The mean BMI was 32.3 kg/m^2.

At week 26, treatment with mealtime LYUMJEV provided a mean reduction of HbA1c from baseline that met the pre-specified non-inferiority margin (0.4%) compared to mealtime HUMALOG (see Table 9). Insulin doses were similar in both treatment groups at baseline and at 26 weeks.

Table 9. Results from Study PRONTO-T2D: 26 Week Trial of Mealtime LYUMJEV Compared with Mealtime HUMALOG, both in Combination with Basal Insulin in Adults with Type 2 Diabetes
 | Mealtime LYUMJEV + basal insulin | Mealtime HUMALOG + basal insulin
Number of randomized subjects (N) | 336 | 337
HbA1c (%)a
Baseline mean | 7.3 | 7.3
Adjusted mean change from baselineb | -0.36 | -0.38
Estimated treatment difference versus HUMALOG [95% CI]c | 0.03 [-0.08, 0.13]
a Analysis population: all randomized subjects regardless of adherence to treatment or availability of post-baseline assessment. Missing data at Week 26 were imputed by return to baseline approach. At week 26, primary efficacy assessment was missing for 4.8% of subjects for mealtime LYUMJEV and for 4.5% mealtime HUMALOG.
b Least-squares (LS) mean from ANCOVA adjusted for baseline value and other stratification factors.
c Tested for non-inferiority.

14.4 Adults with Type 1 Diabetes – Continuous Subcutaneous Insulin Infusion (CSII)

PRONTO-Pump-2 (NCT03830281) was a 16 week randomized (1:1), active controlled, treat-to-target, multinational trial that evaluated the efficacy of LYUMJEV in 432 adult patients with type 1 diabetes currently using continuous subcutaneous insulin infusion. Patients were randomized to either blinded LYUMJEV (N=215) or blinded HUMALOG (N= 217). Mealtime LYUMJEV or HUMALOG boluses were initiated 0 to 2 minutes before the meal.

Patients had a mean age of 46 years; mean duration of diabetes of 26 years; 45% were male; race: 95% White, 3% Black or African American, and 0.5% Asian. Eight percent of the randomized patients were Hispanic. The mean BMI was 27.1 kg/m^2.

At week 16, treatment with LYUMJEV provided a mean reduction in HbA1c that met the pre-specified non-inferiority margin (0.4%) compared to mealtime HUMALOG (see Table 10). Total daily insulin doses were similar for both treatment groups at baseline and at 16 weeks.

Table 10. Results from Study PRONTO-Pump-2: 16 Week Trial of LYUMJEV compared with HUMALOG in Adults with Type 1 Diabetes
 | LYUMJEV | HUMALOG
Number of randomized subjects (N) | 215 | 217
HbA1c (%)a
Baseline mean | 7.6 | 7.5
Adjusted mean change from baselineb | -0.06 | -0.09
Estimated treatment difference versus HUMALOG [95% CI]c | 0.03 [-0.05, 0.11]
a Analysis population: all randomized subjects regardless of adherence to treatment or availability of post-baseline assessment. Missing data at Week 16 were imputed by return to baseline approach. At week 16, primary efficacy assessment was missing for 7% and 4.6% of subjects, for LYUMJEV and HUMALOG, respectively.
b Least-squares (LS) mean from ANCOVA adjusted for baseline value and other stratification factors.
c Tested for non-inferiority.

14.5 Pediatric Patients with Type 1 Diabetes

PRONTO-Peds (NCT03740919) was a 26-week, randomized (2:2:1), active controlled, treat-to-target, multinational trial that evaluated the efficacy of LYUMJEV in 716 pediatric patients with type 1 diabetes. Patients were randomized to either blinded mealtime LYUMJEV (N=280), blinded mealtime HUMALOG (N=298), or open-label postmeal LYUMJEV (N=138), all in combination with basal insulin (insulin glargine, insulin degludec or insulin detemir). Mealtime LYUMJEV or HUMALOG was injected 0 to 2 minutes before the meal and postmeal LYUMJEV was injected within 20 minutes after the start of the meal.

Patients had a mean age of 12 years (3-17 years); 51% were male; race: 89% White, 6% Asian, and 2% Black or African American. In the U.S. subpopulation in this trial, 24% of the randomized patients were Hispanic. The mean BMI was 20.4 kg/m^2 and the mean duration of diabetes was 5 years.

At week 26, treatment with mealtime LYUMJEV provided a mean change in HbA1c that met the pre-specified non-inferiority margin (0.4%) (see Table 11). In addition, postmeal LYUMJEV met the prespecified non-inferiority margin (0.4%) compared to mealtime HUMALOG. Insulin doses were similar in all treatment groups at baseline and at 26 weeks.

Table 11. Results from Study PRONTO-Peds: 26 Week Trial of Mealtime LYUMJEV and Postmeal LYUMJEV compared with Mealtime HUMALOG, all in Combination with Basal Insulin in Pediatric Patients with Type 1 Diabetes
 | Mealtime LYUMJEV + basal insulin | Mealtime HUMALOG + basal insulin | Postmeal LYUMJEV + basal insulin
Number of randomized subjects (N) | 280 | 298 | 138
HbA1c (%) (mean) a
Baseline | 7.8 | 7.8 | 7.8
Adjusted mean change from baselineb | 0.06 | 0.06 | 0.06
Estimated treatment difference versus HUMALOG [95% CI]c | -0.01 [-0.15, 0.14] |  | -0.00 [-0.18, 0.18]
a Analysis population: all randomized subjects regardless of adherence to treatment or availability of post-baseline assessment. Missing data at Week 26 were imputed by return to baseline approach. At week 26, primary efficacy assessment was missing for 5.4%, 7.1%, and 5.1% of subjects, for mealtime LYUMJEV, mealtime HUMALOG, and postmeal LYUMJEV, respectively.
b Least-squares (LS) mean from ANCOVA adjusted for baseline value and other stratification factors.
c Tested for non-inferiority.

16 HOW SUPPLIED/STORAGE AND HANDLING

16.1 How Supplied

LYUMJEV (insulin lispro-aabc) injection is a clear and colorless solution available as shown in Table 12.

Table 12. How Supplied
LYUMJEV | NDC Number | Concentration | Total Units in Presentation | Dose Increment | Package Size
U-100 multiple-dose 10 mL vial | 0002-7728-01 | 100 units/mL | 1,000 units | n/a | 1 vial
U-100 single-patient-use 3 mL cartridgea | 0002-7726-05 | 100 units/mL | 300 units | n/a | 5 cartridges
U-100 single-patient-use 3 mL KwikPen | 0002-8207-05 | 100 units/mL | 300 units | 1 unit | 5 pens
U-100 single-patient-use 3 mL Junior KwikPen | 0002-8351-05 | 100 units/mL | 300 units | 0.5 unit | 5 pens
U-100 single-patient-use 3 mL Tempo Penb | 0002-8235-05 | 100 units/mL | 300 units | 1 unit | 5 pens
U-200 single-patient-use 3 mL KwikPen | 0002-8228-27 | 200 units/mL | 600 units | 1 unit | 2 pens
a 3 mL cartridge is for use in Eli Lilly and Company's HumaPen® Luxura® HD insulin delivery device. Patients need to check their device manual to determine if the LYUMJEV cartridge is compatible for use in other devices.
b Tempo Pen contains a component that allows for data connectivity when used with a compatible transmitter.

16.2 Storage and Handling

- Dispense in the original sealed carton with the enclosed Instructions for Use.
- Refrigerate unopened LYUMJEV vials, pens, and cartridges between 36°F to 46°F (2°C to 8°C) until time of use and keep in the original carton to protect from light. Do not freeze or use LYUMJEV if it has been frozen. Do not expose to direct heat. Discard opened or unopened LYUMJEV vials, pens, and cartridges stored at room temperature below 86°F (30°C) after 28 days.

The storage conditions for vials, pens, and cartridges are summarized in Table 13.

Table 13. Storage Conditions for Vials, Pens, and Cartridges
LYUMJEV Presentation | Not In-use (Unopened) |  | In-use (Opened)
 | Room Temperature (below 86°F [30°C]) | Refrigerated (36°F to 46°F [2°C to 8°C]) | Room Temperature (below 86°F [30°C]) | Refrigerated (36°F to 46°F [2°C to 8°C])
10 mL viala,b | 28 days | Until expiration date | 28 days | 28 days
3 mL cartridgeb | 28 days | Until expiration date | 28 days | Do not refrigerate
3 mL LYUMJEV KwikPen (U-100 and U-200)b | 28 days | Until expiration date | 28 days | Do not refrigerate
3 mL LYUMJEV Junior KwikPenb | 28 days | Until expiration date | 28 days | Do not refrigerate
3 mL LYUMJEV Tempo Penb | 28 days | Until expiration date | 28 days | Do not refrigerate
a In-use (opened) vials, whether or not refrigerated, must be used within 28 days.
b When stored at room temperature, LYUMJEV can only be used for a total of 28 days including both not in-use (unopened) and in-use (opened) storage time.

Storage of LYUMJEV in Insulin Pump

Change the LYUMJEV U-100 in the pump reservoir at least every 9 days, or according to the pump user manual, whichever is shorter, or after exposure to temperatures that exceed 98.6°F (37°C).

Storage of LYUMJEV in Intravenous Infusion Fluids

Diluted LYUMJEV may be stored for up to 4 days when refrigerated at 36°F to 46°F (2°C to 8°C) until time of use. The same solution may be stored up to 12 hours at room temperature at 68°F to 77°F (20°C to 25°C) [see Dosage and Administration (2.2)].

17 PATIENT COUNSELING INFORMATION

Advise the patient to read the FDA-Approved Patient Labeling (Patient Information and Instructions for Use).

Never Share a LYUMJEV Prefilled Pen, Cartridge, or Syringe Between Patients

Advise patients that they must never share a LYUMJEV prefilled pen or cartridge with another person, even if the needle is changed. Advise patients using LYUMJEV vials not to share needles or syringes with another person. Sharing poses a risk for transmission of blood-borne pathogens [see Warnings and Precautions (5.1)].

Hyperglycemia or Hypoglycemia

Inform patients that hypoglycemia is the most common adverse reaction with insulin. Instruct patients on self-management procedures including glucose monitoring, proper injection technique, and management of hypoglycemia and hyperglycemia, especially at initiation of LYUMJEV therapy. Instruct patients on handling of special situations such as intercurrent conditions (illness, stress, or emotional disturbances), an inadequate or skipped insulin dose, inadvertent administration of an increased insulin dose, inadequate food intake, and skipped meals. Instruct patients on the management of hypoglycemia.

Inform patients that their ability to concentrate and react may be impaired as a result of hypoglycemia. Advise patients who have frequent hypoglycemia or reduced or absent warning signs of hypoglycemia to use caution when driving or operating machinery [see Warnings and Precautions (5.3)].

Advise patients that changes in insulin regimen can predispose to hyperglycemia or hypoglycemia and that changes in insulin regimen should be made under close medical supervision [see Warnings and Precautions (5.2)].

Hypoglycemia due to Medication Errors

Instruct patients to always check the insulin label before each injection to avoid mix-ups between insulin products.

Inform patients that LYUMJEV U-200 contains 2 times as much insulin per mL as LYUMJEV U-100. The LYUMJEV U-200 KwikPen dose window shows the number of units of LYUMJEV U-200 to be injected so no dose conversion is required [see Dosage and Administration (2.1)].

Instruct patients to not transfer LYUMJEV U-200 from the LYUMJEV U-200 KwikPen to a syringe [see Warnings and Precautions (5.4)].

Hypersensitivity Reactions

Advise patients that hypersensitivity reactions have occurred with LYUMJEV. Inform patients on the symptoms of hypersensitivity reactions [see Warnings and Precautions (5.6)].

Instructions for Patients Using Continuous Subcutaneous Infusion (Insulin Pump)

- Do not use LYUMJEV U-200 in an insulin pump.
- Train patients in intensive insulin therapy with multiple injections and in the function of their pump and pump accessories.
- Instruct patients to follow healthcare provider recommendations when setting pump basal rates and bolus settings.
- Refer to the continuous subcutaneous infusion pump user manual to see if LYUMJEV can be used with the pump. See recommended reservoir and infusion sets in the insulin pump user manual.
- Instruct patients to replace insulin in the reservoir at least every 9 days, or according to the pump user manual whichever is shorter. By following this schedule, patients avoid insulin degradation, infusion set occlusion, and loss of the insulin preservative.
- Instruct patients to discard insulin exposed to temperatures higher than 98.6°F (37°C).
- Instruct patients to inform healthcare provider and select a new site for infusion if infusion site becomes erythematous, pruritic, or thickened.
- Instruct patients on the risk of rapid hyperglycemia and ketosis due to pump malfunction, infusion set occlusion, leakage, disconnection or kinking, and degraded insulin. Instruct patients on the risk of hypoglycemia from pump malfunction. If these problems cannot be promptly corrected, instruct patients to resume therapy with subcutaneous insulin injection and contact their healthcare provider [see Warnings and Precautions (5) and How Supplied/Storage and Handling (16.2)].

Eli Lilly and Company, Indianapolis, IN 46285, USA

US License No. 1891

Copyright © 2020, 2022, Eli Lilly and Company. All rights reserved.

LUM-0003-USPI-20221014

LYUMJEV PATIENT PACKAGE INSERT

Patient Information
LYUMJEV® (LOOM-jehv)
(insulin lispro-aabc)
injection, for subcutaneous or intravenous use

Do not share your LYUMJEV with other people, even if the needle has been changed. You may give other people a serious infection, or get a serious infection from them.

What is LYUMJEV?

- LYUMJEV is a man-made fast-acting insulin used to control high blood sugar in adults and children with diabetes mellitus.

Do not take LYUMJEV if you:

- are having an episode of low blood sugar (hypoglycemia).
- have an allergy to insulin lispro-aabc or any of the ingredients in LYUMJEV. See the end of this Patient Information leaflet for a complete list of ingredients in LYUMJEV.

Before taking LYUMJEV, tell your healthcare provider about all of your medical conditions, including if you:

- have kidney or liver problems.
- take any other medicines, especially ones called thiazolidinediones (TZDs).
- have heart failure or other heart problems. If you have heart failure, it may get worse while you take TZDs with LYUMJEV.
- are pregnant or plan to become pregnant. Talk with your healthcare provider about the best way to control your blood sugar if you plan to become pregnant or while you are pregnant.
- are breastfeeding or plan to breastfeed. It is not known if LYUMJEV passes into your breast milk. You and your healthcare provider should decide if you will take LYUMJEV while you breastfeed.

Tell your healthcare provider about all the medicines you take, including prescription and over-the-counter medicines, vitamins, and herbal supplements.
Before you start taking LYUMJEV, talk to your healthcare provider about low blood sugar and how to manage it.

How should I take LYUMJEV?

- Read the Instructions for Use that come with your LYUMJEV.
- Take LYUMJEV exactly as your healthcare provider tells you to. Your healthcare provider will tell you how much LYUMJEV to take and when to take it.
- LYUMJEV starts acting fast. Inject LYUMJEV at the beginning of a meal or within 20 minutes after you start eating a meal.
- Know the type and strength of insulin you take. Do not change the type or amount of insulin you take unless your healthcare provider tells you to. The amount of insulin and the best time for you to take your insulin may need to change if you take different types of insulin.
- Check your insulin label each time you give your injection to make sure you are using the correct insulin.
- Check your blood sugar levels. Ask your healthcare provider what your blood sugars should be and when you should check your blood sugar level.
- LYUMJEV comes in U-100 (100 units/mL) and U-200 (200 units/mL) insulin strengths. LYUMJEV U-200 contains 2 times as much insulin (200 units/mL) in 1 mL as LYUMJEV U-100 (100 units/mL).
- LYUMJEV U-100 and LYUMJEV U-200 can be injected under the skin (subcutaneously) of your stomach area, buttocks, upper legs, or upper arms.
- LYUMJEV U-100 can be given by continuous infusion under the skin (subcutaneously) through an insulin pump into an area of your body recommended in the instructions that come with your insulin pump. LYUMJEV U-200 cannot be given through an insulin pump.
- LYUMJEV U-100 can also be given in your vein (intravenously) by your healthcare provider. LYUMJEV U-200 cannot be given in your vein.
- Change (rotate) your injection sites within the area you choose with each dose to reduce your risk of getting pits in skin or thickened skin (lipodystrophy) and skin with lumps (localized cutaneous amyloidosis) at the injection sites.
  - Do not use the exact same spot for each injection.
  - Do not inject where the skin has pits, is thickened, or has lumps.
  - Do not inject where the skin is tender, bruised, scaly or hard, or into scars or damaged skin.
- If you miss a dose of LYUMJEV, monitor your blood sugar levels to decide if an insulin dose is needed. Continue with your regular dosing schedule at the next meal.
- LYUMJEV comes in a vial, single-patient-use prefilled pen, or in a cartridge. Do not use a syringe to remove LYUMJEV from your single-patient-use prefilled pen or cartridge.

Keep LYUMJEV and all medicines out of the reach of children.

Your dose of LYUMJEV may need to change because of:
a change in level of physical activity or exercise, weight gain or loss, increased stress, illness, change in diet, or because of other medicines you take.

What should I avoid while taking LYUMJEV?
While taking LYUMJEV do not:

- drive or operate heavy machinery, until you know how LYUMJEV affects you.
- drink alcohol or take other medicines that contain alcohol.

What are the possible side effects of LYUMJEV?
LYUMJEV may cause serious side effects that can lead to death, including:

- low blood sugar (hypoglycemia). Signs and symptoms that may indicate low blood sugar include: dizziness or light-headedness, sweating, confusion, headache, blurred vision, slurred speech, shakiness, fast heartbeat, hunger, anxiety, irritability, or mood changes.
- low potassium in your blood (hypokalemia).
- serious allergic reactions (whole body allergic reaction). Get emergency medical help right away, if you have any of these symptoms of a severe allergic reaction: a rash over your whole body, trouble breathing, a fast heartbeat, swelling of your face, tongue, or throat, sweating, or feeling faint.
- heart failure. Taking certain diabetes pills called thiazolidinediones (TZDs) with LYUMJEV may cause heart failure in some people. This can happen even if you have never had heart failure or heart failure problems before. If you already have heart failure it may get worse while you take TZDs with LYUMJEV. Your healthcare provider should monitor you closely while you are taking TZDs with LYUMJEV. Tell your healthcare provider if you have any new or worse symptoms of heart failure including: shortness of breath, swelling of your ankles or feet, or sudden weight gain. Treatment with TZDs and LYUMJEV may need to be adjusted or stopped by your healthcare provider if you have new or worse heart failure.
- sudden onset of high blood sugar (hyperglycemia) and high amounts of ketones in the blood or urine (ketoacidosis) due to insulin pump problems. If LYUMEV is given through an insulin pump and the pump is not working the right way or in case of handling errors, you may not get the right amount of insulin, which can cause a sudden onset of high blood sugar and high amounts of ketones in the blood or urine.

Get emergency medical help if you have:

- trouble breathing, shortness of breath, fast heartbeat, swelling of your face, tongue or throat, sweating, extreme drowsiness, dizziness, or confusion.

The most common side effects of LYUMJEV include:

- low blood sugar (hypoglycemia)
- allergic reactions
- rash
- itching (pruritus)

- thickening or pits at the injection or infusion site (lipodystrophy)
- weight gain

- reactions or pain at the site of injection or at the site of infusion with insulin pump use (treprostinil sodium and sodium citrate dihydrate are inactive ingredients in LYUMJEV that have been known to cause reactions and pain at the infusion and injection sites in other non-insulin medicines)

These are not all the possible side effects of LYUMJEV. Call your doctor for medical advice about side effects. You may report side effects to FDA at 1-800-FDA-1088.

General information about the safe and effective use of LYUMJEV.
Medicines are sometimes prescribed for purposes other than those listed in a Patient Information leaflet. Do not take LYUMJEV for a condition for which it was not prescribed. Do not give LYUMJEV to other people, even if they have the same symptoms that you have. It may harm them.
You can ask your pharmacist or healthcare provider for information about LYUMJEV that is written for health professionals.

What are the ingredients in LYUMJEV?
Active ingredient: insulin lispro-aabc
Inactive ingredients: glycerol, magnesium chloride hexahydrate, metacresol, sodium citrate dihydrate, treprostinil sodium, zinc oxide (zinc ion), and Water for Injection, USP

LYUMJEV® is a registered trademark of Eli Lilly and Company.
Eli Lilly and Company Indianapolis, IN 46285, USA
US License Number 1891
Copyright © 2020, 2022, Eli Lilly and Company. All rights reserved.
For more information, go to www.lilly.com or call 1-800-545-5979.

This Patient Information has been approved by the U.S. Food and Drug Administration

Revised: October 2022

LUM-0003-PPI-20221014

LYUMJEV VIAL U-100 INSTRUCTIONS FOR USE

Instructions for Use

LYUMJEV™ (LOOM-jehv)

(insulin lispro-aabc) injection

for subcutaneous use

(100 units/mL, 10 mL multiple-dose vial)

Read the Instructions for Use before you start taking LYUMJEV and each time you get a new vial. There may be new information. This information does not take the place of talking to your healthcare provider about your medical condition or your treatment.

Do not share your syringes or needles with other people. You may give other people a serious infection or get a serious infection from them.

Supplies needed to give your injection

- a multiple-dose LYUMJEV vial
- a U-100 insulin syringe and needle (Becton, Dickinson and Company syringes and needles recommended)
- 2 alcohol swabs
- gauze (optional)
- 1 sharps container for throwing away used syringes and needles. See “Disposing of used syringes and needles” at the end of these instructions.

Preparing your LYUMJEV dose

- Wash your hands with soap and water.
- Check the LYUMJEV label to make sure you are taking the right type of insulin. This is especially important if you use more than 1 type of insulin.
- LYUMJEV should look clear and colorless. Do not use LYUMJEV if it is thick, cloudy, or colored, or if you see lumps or particles in it.
- Do not use LYUMJEV past the expiration date printed on the label or 28 days after you first use it.
- Always use a new syringe and needle for each injection to prevent infections and blocked needles.
- Do not mix LYUMJEV U-100 with other insulins.

Step 1:
If you are using a new vial, pull off the plastic protective cap, but do not remove the rubber stopper.

Step 2:
Wipe the rubber stopper with an alcohol swab.

Step 3:
Remove the needle shield from the syringe by pulling the needle shield straight off. Hold the syringe with the needle pointing up. Pull down on the plunger until the plunger tip reaches the line for the number of units for your prescribed dose.

(Example Dose: 20 units shown)

Step 4:
Push the needle through the rubber stopper of the vial.

Step 5:
Push the plunger all the way in. This puts air into the vial.

Step 6:
Turn the vial and syringe upside down and slowly pull the plunger down until the plunger tip is a few units past the line for your prescribed dose.

(Example Dose: 20 units, plunger is shown at 24 units)

If there are air bubbles, tap the syringe gently a few times to let any air bubbles rise to the top.

Step 7:
Slowly push the plunger up until the plunger tip reaches the line for your prescribed dose.
Check the syringe to make sure that you have the right dose.

(Example Dose: 20 units shown)

Step 8:
Pull the syringe out of the rubber stopper of the vial.

Giving your LYUMJEV injection with a syringe

- Inject your insulin exactly as your healthcare provider has shown you. Your healthcare provider should tell you if you should pinch the skin before injecting.
- LYUMJEV starts acting fast, so give your injection at the start of a meal or within 20 minutes after you start a meal.
- Change (rotate) your injection sites within the area you choose for each dose to reduce your risk of getting lipodystrophy (pits in skin or thickened skin) and localized cutaneous amyloidosis (skin with lumps) at the injection sites.
- Do not use the exact same spot for each injection.
- Do not inject where the skin has pits, is thickened, or has lumps.
- Do not inject where the skin is tender, bruised, scaly or hard, or into scars or damaged skin.

Step 9:
Choose your injection site.
LYUMJEV is injected under the skin (subcutaneously) of your stomach area (abdomen), buttocks, upper legs, or upper arms.
Wipe your skin with an alcohol swab, and let your skin dry before you inject your dose.

Step 10:
Insert the needle into your skin.

Step 11:
Push down on the plunger to inject your dose.
The needle should stay in your skin for at least 5 seconds after pushing down on the plunger to make sure you have injected all of your insulin dose.

Step 12:
Pull the needle out of your skin.

- If you see blood after you take the needle out of your skin, press the injection site with a piece of gauze or an alcohol swab. Do not rub the area.
- Do not recap the needle. Recapping the needle can lead to a needle stick injury.

Giving your LYUMJEV using an insulin pump

- If you have been prescribed an insulin pump, check the pump manufacturer's user manual to see if LYUMJEV can be used with the pump.
- LYUMJEV should be given into an area of your body recommended in the instructions that come with your insulin pump.
- Change LYUMJEV in the pump reservoir at least every 9 days or according to the pump user manual, whichever is shorter, even if you have not used all of the insulin.
- Change (rotate) your insertion sites within the area you choose for each insertion to reduce your risk of getting lipodystrophy (pits in skin or thickened skin) and localized cutaneous amyloidosis (skin with lumps) at the insertion sites. Do not insert into the exact same spot for each insertion. Do not insert where the skin has pits, is thickened, or has lumps. Do not insert where the skin is tender, bruised, scaly or hard, or into scars or damaged skin.
- Call your healthcare provider and choose a new infusion site if the skin at the infusion site becomes red, itchy, or thickened.
- Your healthcare provider should provide recommendations for appropriate pump basal and meal-time infusion rates. Call your healthcare provider if you have any questions about using the insulin pump.
- Do not dilute or mix LYUMJEV with any other type of insulin in your insulin pump.
- You should be trained on how to give insulin by injection and have an alternative insulin delivery system in case of pump failure.

Disposing of used syringes and needles

- Put your used syringes and needles in a FDA-cleared sharps disposal container right away after use. Do not throw away (dispose of) loose syringes and needles in your household trash.
- If you do not have a FDA-cleared sharps disposal container, you may use a household container that is:
  - made of a heavy-duty plastic,
  - can be closed with a tight-fitting, puncture-resistant lid, without sharps being able to come out,
  - upright and stable during use,
  - leak-resistant, and
  - properly labeled to warn of hazardous waste inside the container.
- When your sharps disposal container is almost full, you will need to follow your community guidelines for the right way to dispose of your sharps disposal container. There may be state or local laws about how you should throw away used syringes and needles. For more information about safe sharps disposal, and for specific information about sharps disposal in the state that you live in, go to the FDA's website at: http://www.fda.gov/safesharpsdisposal.
- Do not dispose of your used sharps disposal container in your household trash unless your community guidelines permit this. Do not recycle your used sharps disposal container.

How should I store LYUMJEV?

All not in-use (unopened) vials:

- Store all not in-use (unopened) vials in the refrigerator at 36°F to 46°F (2°C to 8°C).
- Do not freeze. Do not use if LYUMJEV has been frozen.
- Keep away from direct heat and light.
- Not in-use (unopened) vials can be used until the expiration date on the carton and label, if they have been stored in the refrigerator.
- Not in-use (unopened) vials should be thrown away after 28 days, if they are stored at room temperature.

After vials have been in-use (opened):

- Store in-use (opened) vials in the refrigerator or at room temperature below 86°F (30°C) for up to 28 days.
- Keep vials away from direct heat and light.
- Throw away all in-use (opened) vials after 28 days of use, even if there is insulin left in the vial.

LYUMJEV in an insulin pump:

- Throw away LYUMJEV in the pump reservoir if it has been exposed to temperatures higher than 98.6°F (37°C).

Keep LYUMJEV vials, syringes, needles and all medicines out of the sight and reach of children.

If you have any questions or problems with your LYUMJEV, contact Lilly at 1-800-Lilly-Rx (1-800-545-5979) or call your healthcare provider for help. For more information on LYUMJEV and insulin, go to www.lyumjev.com.

Scan this code to launch

www.lyumjev.com

Manufactured by:
Eli Lilly and Company
Indianapolis, IN 46285, USA
US License Number 1891

LYUMJEV™ is a trademark of Eli Lilly and Company.

Copyright © 2020, 2021, Eli Lilly and Company. All rights reserved.

This Instructions for Use has been approved by the U.S. Food and Drug Administration.

Revised: August 2021
LUMVL-0002-IFU-20210813

LYUMJEV KWIKPEN U-100 INSTRUCTIONS FOR USE

Instructions for Use

LYUMJEV™ KwikPen® (LOOM-jehv)

(insulin lispro-aabc)

injection, for subcutaneous use

3 mL single-patient-use pen

100 units/mL

Read the Instructions for Use before you start taking LYUMJEV™ and each time you get another LYUMJEV KwikPen. There may be new information. This information does not take the place of talking to your healthcare provider about your medical condition or your treatment.

Do not share your LYUMJEV KwikPen with other people, even if the needle has been changed. Do not reuse or share needles with other people. You may give other people a serious infection or get a serious infection from them.

LYUMJEV KwikPen (“Pen”) is a disposable single-patient-use prefilled pen containing 300 units of LYUMJEV.

- Your healthcare provider will tell you how many units to give as your dose and how to inject your prescribed dose of insulin.
- You can give yourself more than 1 dose from the Pen.
- Each turn of the dose knob dials 1 unit of insulin. You can give from 1 to 60 units in a single injection.
- If your dose is more than 60 units, you will need to give yourself more than 1 injection. Always check the number in the dose window to make sure you dialed the correct dose.
- The plunger only moves a little with each injection, and you may not notice that it moves. The plunger will only reach the end of the cartridge when you have used all 300 units in the Pen.

People who are blind or have vision problems should not use the Pen without help from a person trained to use the Pen.

How to recognize your LYUMJEV KwikPen

- Pen color: | Taupe
- Dose Knob: | Blue, with raised ridges on side
- Label: | Blue and white

Supplies needed to give your injection

- LYUMJEV KwikPen, 100 units/mL
- KwikPen compatible needle (Becton, Dickinson and Company Pen needles recommended)
- Alcohol swab
- Gauze (optional)

Preparing your Pen

- Wash your hands with soap and water.
- Check the Pen to make sure you are taking the right type of insulin. This is especially important if you use more than 1 type of insulin.
- Do not use your Pen past the expiration date printed on the label or for more than 28 days after you first start using the Pen.
- Always use a new needle for each injection to help prevent infections and blocked needles.

Step 1:

- Pull the Pen cap straight off.
  - Do not remove the Pen label.
- Wipe the rubber seal with an alcohol swab.

Step 2:

- Check the liquid in the Pen.
- LYUMJEV should look clear and colorless. Do not use if it is cloudy, colored, or has particles or clumps in it.

Step 3:

- Select a new needle.
- Pull off the paper tab from the outer needle shield.

Step 4:

- Push the capped needle straight onto the Pen and twist the needle on until it is tight.

Step 5:

- Pull off the outer needle shield. Do not throw it away.
- Pull off the inner needle shield and throw it away.

Priming your Pen

Prime before each injection.

- Priming your Pen means removing the air from the needle and cartridge that may collect during normal use and ensures that your Pen is working correctly.
- If you do not prime before each injection, you may get too much or too little insulin.

Step 6:

- To prime your Pen, turn the dose knob to select 2 units.

Step 7:

- Hold your Pen with the needle pointing up. Tap the cartridge holder gently to collect air bubbles at the top.

Step 8:

- Continue holding your Pen with the needle pointing up. Push the dose knob in until it stops and “0” is seen in the dose window. Hold the dose knob in and count to 5 slowly.

You should see insulin at the tip of the needle.

- If you do not see insulin, repeat priming steps 6 to 8, but not more than 4 times.
- If you still do not see insulin, change the needle and repeat priming steps 6 to 8.

Small air bubbles are normal and will not affect your dose.

Selecting your dose

- You can give from 1 to 60 units in a single injection.
- If your dose is more than 60 units, you will need to give more than 1 injection.
  - If you need help with dividing up your dose the right way, ask your healthcare provider.
  - Use a new needle for each injection and repeat the priming steps.

Step 9:

- Turn the dose knob to select the number of units you need to inject. The dose indicator should line up with your dose.
  - The Pen dials 1 unit at a time.
  - The dose knob clicks as you turn it.
  - Do not dial your dose by counting the clicks. You may dial the wrong dose. This may lead to you getting too much insulin or not enough insulin.
  - The dose can be corrected by turning the dose knob in either direction until the correct dose lines up with the dose indicator.
  - The even numbers are printed on the dial. The example to the right shows 12 units in the dose window.
  - The odd numbers, after the number 1, are shown as full lines between the numbers. The example to the right shows 25 units in the dose window.
- Always check the number in the dose window to make sure you have dialed the correct dose.

Example: 12 units shown in the dose window
Example: 25 units shown in the dose window

- The Pen will not let you dial more than the number of units left in the Pen.
- If you need to inject more than the number of units left in the Pen, you may either:
  - inject the amount left in your Pen and then use a new Pen to give the rest of your dose,
    or
  - get a new Pen and inject the full dose.
- It is normal to see a small amount of insulin left in the Pen that you cannot inject.

Giving your injection

- Inject your insulin as your healthcare provider has shown you.
- Change (rotate) your injection sites within the area you choose for each dose to reduce your risk of getting lipodystrophy (pits in skin or thickened skin) and localized cutaneous amyloidosis (skin with lumps) at the injection sites.
- Do not use the exact same spot for each injection.
- Do not inject where the skin has pits, is thickened, or has lumps.
- Do not inject where the skin is tender, bruised, scaly or hard, or into scars or damaged skin.
- Do not try to change your dose while injecting.

Step 10:

- Choose your injection site.
  LYUMJEV is injected under the skin (subcutaneously) of your stomach area, buttocks, upper legs or upper arms.
- Wipe your skin with an alcohol swab, and let your skin dry before you inject your dose.

Step 11:

- Insert the needle into your skin.
- Push the dose knob all the way in.

- Continue to hold the dose knob in and slowly count to 5 before removing the needle.

Do not try to inject your insulin by turning the dose knob. You will not receive your insulin by turning the dose knob.

Step 12:

- Pull the needle out of your skin.
  - A drop of insulin at the needle tip is normal. It will not affect your dose.
- Check the number in the dose window.
  - If you see “0” in the dose window, you have received the full amount you dialed.
  - If you do not see “0” in the dose window, you did not receive your full dose. Do not redial. Insert the needle into your skin and finish your injection.
  - If you still do not think you received the full amount you dialed for your injection, do not start over or repeat that injection. Monitor your blood glucose as instructed by your healthcare provider.
  - If you normally need to give 2 injections for your full dose, be sure to give your second injection.

The plunger only moves a little with each injection, and you may not notice that it moves.
If you see blood after you take the needle out of your skin, press the injection site lightly with a piece of gauze or an alcohol swab. Do not rub the area.

After your injection

Step 13:

- Carefully replace the outer needle shield.

Step 14:

- Unscrew the capped needle and throw it away (see Disposing of Pens and needles section).
- Do not store the Pen with the needle attached to prevent leaking, blocking the needle, and air from entering the Pen.

Step 15:

- Replace the Pen cap by lining up the cap clip with the dose indicator and pushing straight on.

Disposing of Pens and needles

- Put your used needles in a FDA-cleared sharps disposal container right away after use. Do not throw away (dispose of) loose needles in your household trash.
- If you do not have a FDA-cleared sharps disposal container, you may use a household container that is:
  - made of a heavy-duty plastic,
  - can be closed with a tight-fitting, puncture-resistant lid, without sharps being able to come out,
  - upright and stable during use,
  - leak-resistant, and
  - properly labeled to warn of hazardous waste inside the container.
- When your sharps disposal container is almost full, you will need to follow your community guidelines for the right way to dispose of your sharps disposal container. There may be state or local laws about how you should throw away used needles and syringes. For more information about safe sharps disposal, and for specific information about sharps disposal in the state that you live in, go to the FDA's website at: http://www.fda.gov/safesharpsdisposal
- Do not dispose of your used sharps disposal container in your household trash unless your community guidelines permit this. Do not recycle your used sharps disposal container.
- The used Pen may be discarded in your household trash after you have removed the needle.

Storing your Pen

Unused Pens

- Store unused Pens in the refrigerator at 36°F to 46°F (2°C to 8°C).
- Do not freeze LYUMJEV. Do not use if it has been frozen.
- Unused Pens may be used until the expiration date printed on the label if the Pen has been kept in the refrigerator.

In-use Pen

- Store the Pen you are currently using at room temperature [up to 86°F (30°C)]. Keep away from heat and light.
- Throw away the LYUMJEV KwikPen you are using after 28 days, even if it still has insulin left in it.

General information about the safe and effective use of your Pen

- Keep your Pen and needles out of the sight and reach of children.
- Do not use your Pen if any part looks broken or damaged.
- Always carry an extra Pen in case yours is lost or damaged.

Troubleshooting

- If you cannot remove the Pen cap, gently twist the cap back and forth, and then pull the cap straight off.
- If the dose knob is hard to push:
  - pushing the dose knob more slowly will make it easier to inject.
  - your needle may be blocked. Put on a new needle and prime the Pen.
  - you may have dust, food, or liquid inside the Pen. Throw the Pen away and get a new Pen.

If you have any questions or problems with your LYUMJEV KwikPen, contact Lilly at 1-800-545-5979 or call your healthcare provider for help. For more information on LYUMJEV KwikPen and insulin, go to www.lyumjev.com.

Scan this code to launch

www.lyumjev.com

This Instructions for Use has been approved by the U.S. Food and Drug Administration.

Manufactured by:
Eli Lilly and Company
Indianapolis, IN 46285, USA
US License Number 1891

LYUMJEV™ and LYUMJEV™ KwikPen® are trademarks of Eli Lilly and Company.

Copyright © 2020, Eli Lilly and Company. All rights reserved.

LYUMJEV KwikPen meets the current dose accuracy and functional requirements of ISO 11608-1.

Issued: June 2020

LUMKP-0001-IFU-20200615

LYUMJEV JUNIOR KWIKPEN U-100 INSTRUCTIONS FOR USE

Instructions for Use

LYUMJEV™ Junior KwikPen® (LOOM-jehv)

(insulin lispro-aabc)

injection, for subcutaneous use

3 mL single-patient-use pen

100 units/mL

Read the Instructions for Use before you start taking LYUMJEV™ and each time you get another LYUMJEV Junior KwikPen. There may be new information. This information does not take the place of talking to your healthcare provider about your medical condition or your treatment.

Do not share your LYUMJEV Junior KwikPen with other people, even if the needle has been changed. Do not reuse or share needles with other people. You may give other people a serious infection or get a serious infection from them.

LYUMJEV Junior KwikPen (“Pen”) is a disposable single-patient-use prefilled pen containing 300 units of LYUMJEV.

- Your healthcare provider will tell you how many units to give as your dose and how to inject your prescribed dose of insulin.
- You can give yourself more than 1 dose from the Pen.
- Each turn of the dose knob dials 0.5 (½) unit of insulin. You can give from 0.5 (½) to 30 units in a single injection.
- If your dose is more than 30 units, you will need to give yourself more than 1 injection. Always check the number in the dose window to make sure you dialed the correct dose.
- The plunger only moves a little with each injection, and you may not notice that it moves. The plunger will only reach the end of the cartridge when you have used all 300 units in the Pen.

People who are blind or have vision problems should not use the Pen without help from a person trained to use the Pen.

How to recognize your LYUMJEV Junior KwikPen

- Pen color: | Taupe
- Dose knob: | Peach, with raised ridges on end and side
- Label: | White with a peach color bar, and peach, light blue and dark blue color band

Supplies needed to give your injection

- LYUMJEV Junior KwikPen, 100 units/mL
- KwikPen compatible needle (Becton, Dickinson and Company Pen needles recommended)
- Alcohol swab
- Gauze (optional)

Preparing your Pen

- Wash your hands with soap and water.
- Check the Pen to make sure you are taking the right type of insulin. This is especially important if you use more than 1 type of insulin.
- Do not use your Pen past the expiration date printed on the label or for more than 28 days after you first start using the Pen.
- Always use a new needle for each injection to help prevent infections and blocked needles.

Step 1:

- Pull the Pen cap straight off.
  - Do not remove the Pen label.
- Wipe the rubber seal with an alcohol swab.

Step 2:

- Check the liquid in the Pen.
- LYUMJEV should look clear and colorless. Do not use if it is cloudy, colored, or has particles or clumps in it.

Step 3:

- Select a new needle.
- Pull off the paper tab from the outer needle shield.

Step 4:

- Push the capped needle straight onto the Pen and twist the needle on until it is tight.

Step 5:

- Pull off the outer needle shield. Do not throw it away.
- Pull off the inner needle shield and throw it away.

Priming your Pen

Prime before each injection.

- Priming your Pen means removing the air from the needle and cartridge that may collect during normal use and ensures that your Pen is working correctly.
- If you do not prime before each injection, you may get too much or too little insulin.

Step 6:

- To prime your Pen, turn the dose knob to select 2 units.

Step 7:

- Hold your Pen with the needle pointing up. Tap the cartridge holder gently to collect air bubbles at the top.

Step 8:

- Continue holding your Pen with the needle pointing up. Push the dose knob in until it stops and “0” is seen in the dose window. Hold the dose knob in and count to 5 slowly.

You should see insulin at the tip of the needle.

- If you do not see insulin, repeat priming steps 6 to 8, but not more than 4 times.
- If you still do not see insulin, change the needle and repeat priming steps 6 to 8.

Small air bubbles are normal and will not affect your dose.

Selecting your dose

- You can give from 0.5 (½) to 30 units in a single injection.
- If your dose is more than 30 units, you will need to give more than 1 injection.
  - If you need help with dividing up your dose the right way, ask your healthcare provider.
  - Use a new needle for each injection and repeat the priming steps.
  - If you usually need more than 30 units, ask your healthcare provider if a different LYUMJEV Pen would be better for you.

Step 9:

- Turn the dose knob to select the number of units you need to inject. The dose indicator should line up with your dose.
  - The Pen dials 0.5 (½) unit at a time.
  - The dose knob clicks as you turn it.
  - Do not dial your dose by counting the clicks. You may dial the wrong dose. This may lead to you getting too much insulin or not enough insulin.
  - The dose can be corrected by turning the dose knob in either direction until the correct dose lines up with the dose indicator.
  - The whole unit numbers are printed on the dial. The example to the right shows 4 units in the dose window.
  - The half units are shown as lines between the whole unit numbers. The example to the right shows 10.5 units in the dose window.
- Always check the number in the dose window to make sure you have dialed the correct dose.

Example: 4 units shown in the dose window
Example: 10.5 (10 ½) units shown in the dose window

- The Pen will not let you dial more than the number of units left in the Pen.
- If you need to inject more than the number of units left in the Pen, you may either:
  - inject the amount left in your Pen and then use a new Pen to give the rest of your dose,
    or
  - get a new Pen and inject the full dose.
- It is normal to see a small amount of insulin left in the Pen that you cannot inject.

Giving your injection

- Inject your insulin as your healthcare provider has shown you.
- Change (rotate) your injection sites within the area you choose for each dose to reduce your risk of getting lipodystrophy (pits in skin or thickened skin) and localized cutaneous amyloidosis (skin with lumps) at the injection sites.
- Do not use the exact same spot for each injection.
- Do not inject where the skin has pits, is thickened, or has lumps.
- Do not inject where the skin is tender, bruised, scaly or hard, or into scars or damaged skin.
- Do not try to change your dose while injecting.

Step 10:

- Choose your injection site.
  LYUMJEV is injected under the skin (subcutaneously) of your stomach area, buttocks, upper legs or upper arms.
- Wipe your skin with an alcohol swab, and let your skin dry before you inject your dose.

Step 11:

- Insert the needle into your skin.
- Push the dose knob all the way in.

- Continue to hold the dose knob in and slowly count to 5 before removing the needle.

Do not try to inject your insulin by turning the dose knob. You will not receive your insulin by turning the dose knob.

Step 12:

- Pull the needle out of your skin.
  - A drop of insulin at the needle tip is normal. It will not affect your dose.
- Check the number in the dose window.
  - If you see “0” in the dose window, you have received the full amount you dialed.
  - If you do not see “0” in the dose window, you did not receive your full dose. Do not redial. Insert the needle into your skin and finish your injection.
  - If you still do not think you received the full amount you dialed for your injection, do not start over or repeat that injection. Monitor your blood glucose as instructed by your healthcare provider.
  - If you normally need to give 2 injections for your full dose, be sure to give your second injection.

The plunger only moves a little with each injection, and you may not notice that it moves.
If you see blood after you take the needle out of your skin, press the injection site lightly with a piece of gauze or an alcohol swab. Do not rub the area.

After your injection

Step 13:

- Carefully replace the outer needle shield.

Step 14:

- Unscrew the capped needle and throw it away (see Disposing of Pens and needles section).
- Do not store the Pen with the needle attached to prevent leaking, blocking the needle, and air from entering the Pen.

Step 15:

- Replace the Pen cap by lining up the cap clip with the dose indicator and pushing straight on.

Disposing of Pens and needles

- Put your used needles in a FDA-cleared sharps disposal container right away after use. Do not throw away (dispose of) loose needles in your household trash.
- If you do not have a FDA-cleared sharps disposal container, you may use a household container that is:
  - made of a heavy-duty plastic,
  - can be closed with a tight-fitting, puncture-resistant lid, without sharps being able to come out,
  - upright and stable during use,
  - leak-resistant, and
  - properly labeled to warn of hazardous waste inside the container.
- When your sharps disposal container is almost full, you will need to follow your community guidelines for the right way to dispose of your sharps disposal container. There may be state or local laws about how you should throw away used needles and syringes. For more information about safe sharps disposal, and for specific information about sharps disposal in the state that you live in, go to the FDA's website at: http://www.fda.gov/safesharpsdisposal
- Do not dispose of your used sharps disposal container in your household trash unless your community guidelines permit this. Do not recycle your used sharps disposal container.
- The used Pen may be discarded in your household trash after you have removed the needle.

Storing your Pen

Unused Pens

- Store unused Pens in the refrigerator at 36°F to 46°F (2°C to 8°C).
- Do not freeze LYUMJEV. Do not use if it has been frozen.
- Unused Pens may be used until the expiration date printed on the label if the Pen has been kept in the refrigerator.

In-use Pen

- Store the Pen you are currently using at room temperature [up to 86°F (30°C)]. Keep away from heat and light.
- Throw away the LYUMJEV Junior KwikPen you are using after 28 days, even if it still has insulin left in it.

General information about the safe and effective use of your Pen

- Keep your Pen and needles out of the sight and reach of children.
- Do not use your Pen if any part looks broken or damaged.
- Always carry an extra Pen in case yours is lost or damaged.

Troubleshooting

- If you cannot remove the Pen cap, gently twist the cap back and forth, and then pull the cap straight off.
- If the dose knob is hard to push:
  - pushing the dose knob more slowly will make it easier to inject.
  - your needle may be blocked. Put on a new needle and prime the Pen.
  - you may have dust, food, or liquid inside the Pen. Throw the Pen away and get a new Pen.

If you have any questions or problems with your LYUMJEV Junior KwikPen, contact Lilly at 1-800-545-5979 or call your healthcare provider for help. For more information on LYUMJEV Junior KwikPen and insulin, go to www.lyumjev.com.

Scan this code to launch

www.lyumjev.com

This Instructions for Use has been approved by the U.S. Food and Drug Administration.

Manufactured by:
Eli Lilly and Company
Indianapolis, IN 46285, USA
US License Number 1891

LYUMJEV™ and LYUMJEV™ Junior KwikPen® are trademarks of Eli Lilly and Company.

Copyright © 2020, Eli Lilly and Company. All rights reserved.

LYUMJEV Junior KwikPen meets the current dose accuracy and functional requirements of ISO 11608-1.

Issued: June 2020

LUMJRKP-0001-IFU-20200615

LYUMJEV TEMPO PEN U-100 INSTRUCTIONS FOR USE

Instructions for Use

LYUMJEV™ Tempo Pen™ (LOOM-jehv)

(insulin lispro-aabc)

injection, for subcutaneous use

3 mL single-patient-use pen

100 units/mL

Read the Instructions for Use before you start taking LYUMJEV™ and each time you get another LYUMJEV Tempo Pen. There may be new information. This information does not take the place of talking to your healthcare provider about your medical condition or your treatment.

Do not share your LYUMJEV Tempo Pen with other people, even if the needle has been changed. Do not reuse or share needles with other people. You may give other people a serious infection or get a serious infection from them.

LYUMJEV Tempo Pen (“Pen”) is a disposable single-patient-use prefilled pen containing 300 units of LYUMJEV.

- Your healthcare provider will tell you how many units to give as your dose and how to inject your prescribed dose of insulin.
- You can give yourself more than 1 dose from the Pen.
- Each turn of the dose knob dials 1 unit of insulin. You can give from 1 to 60 units in a single injection.
- If your dose is more than 60 units, you will need to give yourself more than 1 injection. Always check the number in the dose window to make sure you dialed the correct dose.
- The plunger only moves a little with each injection, and you may not notice that it moves. The plunger will only reach the end of the cartridge when you have used all 300 units in the Pen.
- This LYUMJEV Tempo Pen contains a component that allows for data connectivity when used with a compatible transmitter.

People who are blind or have vision problems should not use the Pen without help from a person trained to use the Pen.

How to recognize your LYUMJEV Tempo Pen

- Pen color: | Taupe
- Dose Knob: | Blue, with raised ridges around the entire side
- Label: | Blue and white

Supplies needed to give your injection

- LYUMJEV Tempo Pen, 100 units/mL
- Tempo Pen compatible needle (Becton, Dickinson and Company Pen needles recommended)
- Alcohol swab
- Gauze (optional)

Preparing your Pen

- Wash your hands with soap and water.
- Check the Pen to make sure you are taking the right type of insulin. This is especially important if you use more than 1 type of insulin.
- Do not use your Pen past the expiration date printed on the label or for more than 28 days after you first start using the Pen.
- Always use a new needle for each injection to help prevent infections and blocked needles.

Step 1:

- Pull the Pen cap straight off.
  - Do not remove the Pen label.
- Wipe the rubber seal with an alcohol swab.

Step 2:

- Check the liquid in the Pen.
- LYUMJEV should look clear and colorless. Do not use if it is cloudy, colored, or has particles or clumps in it.

Step 3:

- Select a new needle.
- Pull off the paper tab from the outer needle shield.

Step 4:

- Push the capped needle straight onto the Pen and twist the needle on until it is tight.

Step 5:

- Pull off the outer needle shield. Do not throw it away.
- Pull off the inner needle shield and throw it away.

Priming your Pen

Prime before each injection.

- Priming your Pen means removing the air from the needle and cartridge that may collect during normal use and ensures that your Pen is working correctly.
- If you do not prime before each injection, you may get too much or too little insulin.

Step 6:

- To prime your Pen, turn the dose knob to select 2 units.

Step 7:

- Hold your Pen with the needle pointing up. Tap the cartridge holder gently to collect air bubbles at the top.

Step 8:

- Continue holding your Pen with the needle pointing up. Push the dose knob in until it stops and “0” is seen in the dose window. Hold the dose knob in and count to 5 slowly.

You should see insulin at the tip of the needle.

- If you do not see insulin, repeat priming steps 6 to 8, but not more than 4 times.
- If you still do not see insulin, change the needle and repeat priming steps 6 to 8.

Small air bubbles are normal and will not affect your dose.

Selecting your dose

- You can give from 1 to 60 units in a single injection.
- If your dose is more than 60 units, you will need to give more than 1 injection.
  - If you need help with dividing up your dose the right way, ask your healthcare provider.
  - Use a new needle for each injection and repeat the priming steps.

Step 9:

- Turn the dose knob to select the number of units you need to inject. The dose indicator should line up with your dose.
  - The Pen dials 1 unit at a time.
  - The dose knob clicks as you turn it.
  - Do not dial your dose by counting the clicks. You may dial the wrong dose. This may lead to you getting too much insulin or not enough insulin.
  - The dose can be corrected by turning the dose knob in either direction until the correct dose lines up with the dose indicator.
  - The even numbers are printed on the dial. The example to the right shows 12 units in the dose window.
  - The odd numbers, after the number 1, are shown as full lines between the numbers. The example to the right shows 25 units in the dose window.
- Always check the number in the dose window to make sure you have dialed the correct dose.

Example: 12 units shown in the dose window
Example: 25 units shown in the dose window

- The Pen will not let you dial more than the number of units left in the Pen.
- If you need to inject more than the number of units left in the Pen, you may either:
  - inject the amount left in your Pen and then use a new Pen to give the rest of your dose,
    or
  - get a new Pen and inject the full dose.
- It is normal to see a small amount of insulin left in the Pen that you cannot inject.

Giving your injection

- Inject your insulin as your healthcare provider has shown you.
- Change (rotate) your injection sites within the area you choose for each dose to reduce your risk of getting lipodystrophy (pits in skin or thickened skin) and localized cutaneous amyloidosis (skin with lumps) at the injection sites.
- Do not use the exact same spot for each injection.
- Do not inject where the skin has pits, is thickened, or has lumps.
- Do not inject where the skin is tender, bruised, scaly or hard, or into scars or damaged skin.
- Do not try to change your dose while injecting.

Step 10:

- Choose your injection site.
  LYUMJEV is injected under the skin (subcutaneously) of your stomach area, buttocks, upper legs or upper arms.
- Wipe your skin with an alcohol swab, and let your skin dry before you inject your dose.

Step 11:

- Insert the needle into your skin.
- Push the dose knob all the way in.

- Continue to hold the dose knob in and slowly count to 5 before removing the needle.

Do not try to inject your insulin by turning the dose knob. You will not receive your insulin by turning the dose knob.

Step 12:

- Pull the needle out of your skin.
  - A drop of insulin at the needle tip is normal. It will not affect your dose.
- Check the number in the dose window.
  - If you see “0” in the dose window, you have received the full amount you dialed.
  - If you do not see “0” in the dose window, you did not receive your full dose. Do not redial. Insert the needle into your skin and finish your injection.
  - If you still do not think you received the full amount you dialed for your injection, do not start over or repeat that injection. Monitor your blood glucose as instructed by your healthcare provider.
  - If you normally need to give 2 injections for your full dose, be sure to give your second injection.

The plunger only moves a little with each injection, and you may not notice that it moves.
If you see blood after you take the needle out of your skin, press the injection site lightly with a piece of gauze or an alcohol swab. Do not rub the area.

After your injection

Step 13:

- Carefully replace the outer needle shield.

Step 14:

- Unscrew the capped needle and throw it away (see Disposing of Pens and needles section).
- Do not store the Pen with the needle attached to prevent leaking, blocking the needle, and air from entering the Pen.

Step 15:

- Replace the Pen cap by lining up the cap clip with the dose indicator and pushing straight on.

Disposing of Pens and needles

- Put your used needles in a FDA-cleared sharps disposal container right away after use. Do not throw away (dispose of) loose needles in your household trash.
- If you do not have a FDA-cleared sharps disposal container, you may use a household container that is:
  - made of a heavy-duty plastic,
  - can be closed with a tight-fitting, puncture-resistant lid, without sharps being able to come out,
  - upright and stable during use,
  - leak-resistant, and
  - properly labeled to warn of hazardous waste inside the container.
- When your sharps disposal container is almost full, you will need to follow your community guidelines for the right way to dispose of your sharps disposal container. There may be state or local laws about how you should throw away used needles and syringes. For more information about safe sharps disposal, and for specific information about sharps disposal in the state that you live in, go to the FDA's website at: http://www.fda.gov/safesharpsdisposal
- Do not dispose of your used sharps disposal container in your household trash unless your community guidelines permit this. Do not recycle your used sharps disposal container.
- The used Pen may be discarded in your household trash after you have removed the needle.

Storing your Pen

Unused Pens

- Store unused Pens in the refrigerator at 36°F to 46°F (2°C to 8°C).
- Do not freeze LYUMJEV. Do not use if it has been frozen.
- Unused Pens may be used until the expiration date printed on the label if the Pen has been kept in the refrigerator.

In-use Pen

- Store the Pen you are currently using at room temperature [up to 86°F (30°C)]. Keep away from heat and light.
- Throw away the LYUMJEV Tempo Pen you are using after 28 days, even if it still has insulin left in it.

General information about the safe and effective use of your Pen

- Keep your Pen and needles out of the sight and reach of children.
- Do not use your Pen if any part looks broken or damaged.
- Always carry an extra Pen in case yours is lost or damaged.

Troubleshooting

- If you cannot remove the Pen cap, gently twist the cap back and forth, and then pull the cap straight off.
- If the dose knob is hard to push:
  - pushing the dose knob more slowly will make it easier to inject.
  - your needle may be blocked. Put on a new needle and prime the Pen.
  - you may have dust, food, or liquid inside the Pen. Throw the Pen away and get a new Pen.

If you have any questions or problems with your LYUMJEV Tempo Pen, contact Lilly at 1-800-545-5979 or call your healthcare provider for help. For more information on LYUMJEV Tempo Pen and insulin, go to www.lyumjev.com.

Scan this code to launch

www.lyumjev.com

This Instructions for Use has been approved by the U.S. Food and Drug Administration.

Manufactured by:
Eli Lilly and Company
Indianapolis, IN 46285, USA
US License Number 1891

LYUMJEV™ and LYUMJEV™ Tempo Pen™ are trademarks of Eli Lilly and Company.

Copyright © 2020, Eli Lilly and Company. All rights reserved.

LYUMJEV Tempo Pen meets the current dose accuracy and functional requirements of ISO 11608-1.

Issued: June 2020

LUMTP-0001-IFU-20200615

LYUMJEV KWIKPEN U-200 INSTRUCTIONS FOR USE

Instructions for Use

LYUMJEV™ KwikPen® (LOOM-jehv)

(insulin lispro-aabc)

injection, for subcutaneous use

3 mL single-patient-use pen

200 units/mL

Read the Instructions for Use before you start taking LYUMJEV™ and each time you get another LYUMJEV KwikPen. There may be new information. This information does not take the place of talking to your healthcare provider about your medical condition or your treatment.

Do not share your LYUMJEV KwikPen with other people, even if the needle has been changed. Do not reuse or share needles with other people. You may give other people a serious infection or get a serious infection from them.

LYUMJEV KwikPen (“Pen”) is a disposable single-patient-use prefilled pen containing 600 units of LYUMJEV.

- Your healthcare provider will tell you how many units to give as your dose and how to inject your prescribed dose of insulin.
- You can give yourself more than 1 dose from the Pen.
- Each turn of the dose knob dials 1 unit of insulin. You can give from 1 to 60 units in a single injection.
- If your dose is more than 60 units, you will need to give yourself more than 1 injection. Always check the number in the dose window to make sure you dialed the correct dose.
- The plunger only moves a little with each injection, and you may not notice that it moves. The plunger will only reach the end of the cartridge when you have used all 600 units in the Pen.

LYUMJEV KwikPen is available in two strengths, 100 units/mL and 200 units/mL. Inject LYUMJEV 200 units/mL only with your Pen. Do not transfer insulin from your Pen to a syringe. Syringes will not measure 200 units/mL of insulin correctly. A severe overdose can result, causing very low blood sugar which may put your life in danger.

People who are blind or have vision problems should not use the Pen without help from a person trained to use the Pen.

How to recognize your LYUMJEV KwikPen

- Pen color: | Taupe
- Dose Knob: | Taupe, with raised ridges on side
- Label: | White with a blue color bar and checkerboard design with “200 units per mL (U-200)” in a yellow stripe. Yellow warning on cartridge holder.

Supplies needed to give your injection

- LYUMJEV KwikPen, 200 units/mL
- KwikPen compatible needle (Becton, Dickinson and Company Pen needles recommended)
- Alcohol swab
- Gauze (optional)

Preparing your Pen

- Wash your hands with soap and water.
- Check the Pen to make sure you are taking the right type of insulin. This is especially important if you use more than 1 type of insulin.
- Do not use your Pen past the expiration date printed on the label or for more than 28 days after you first start using the Pen.
- Always use a new needle for each injection to help prevent infections and blocked needles.

Step 1:

- Pull the Pen cap straight off.
  - Do not remove the Pen label.
- Wipe the rubber seal with an alcohol swab.

Step 2:

- Check the liquid in the Pen.
- LYUMJEV should look clear and colorless. Do not use if it is cloudy, colored, or has particles or clumps in it.

Step 3:

- Select a new needle.
- Pull off the paper tab from the outer needle shield.

Step 4:

- Push the capped needle straight onto the Pen and twist the needle on until it is tight.

Step 5:

- Pull off the outer needle shield. Do not throw it away.
- Pull off the inner needle shield and throw it away.

Priming your Pen

Prime before each injection.

- Priming your Pen means removing the air from the needle and cartridge that may collect during normal use and ensures that your Pen is working correctly.
- If you do not prime before each injection, you may get too much or too little insulin.

Step 6:

- To prime your Pen, turn the dose knob to select 2 units.

Step 7:

- Hold your Pen with the needle pointing up. Tap the cartridge holder gently to collect air bubbles at the top.

Step 8:

- Continue holding your Pen with the needle pointing up. Push the dose knob in until it stops and “0” is seen in the dose window. Hold the dose knob in and count to 5 slowly.

You should see insulin at the tip of the needle.

- If you do not see insulin, repeat priming steps 6 to 8, but not more than 8 times.
- If you still do not see insulin, change the needle and repeat priming steps 6 to 8.

Small air bubbles are normal and will not affect your dose.

Selecting your dose

This Pen has been designed to deliver the dose that is shown in the dose window. Dial your usual dose as instructed by your healthcare provider.

- You can give from 1 to 60 units in a single injection.
- If your dose is more than 60 units, you will need to give more than 1 injection.
  - If you need help dividing up your dose the right way, ask your healthcare provider.
  - Use a new needle for each injection and repeat the priming steps.

Step 9:

- Turn the dose knob to select the number of units you need to inject. The dose indicator should line up with your dose.
  - The Pen dials 1 unit at a time.
  - The dose knob clicks as you turn it.
  - Do not dial your dose by counting the clicks. You may dial the wrong dose. This may lead to you getting too much insulin or not enough insulin.
  - The dose can be corrected by turning the dose knob in either direction until the correct dose lines up with the dose indicator.
  - The even numbers are printed on the dial. The example to the right shows 12 units in the dose window.
  - The odd numbers, after the number 1, are shown as full lines between the numbers. The example to the right shows 25 units in the dose window.
- Always check the number in the dose window to make sure you have dialed the correct dose.

Example: 12 units shown in the dose window
Example: 25 units shown in the dose window

- The Pen will not let you dial more than the number of units left in the Pen.
- If you need to inject more than the number of units left in the Pen, you may either:
  - inject the amount left in your Pen and then use a new Pen to give the rest of your dose,
    or
  - get a new Pen and inject the full dose.
- It is normal to see a small amount of insulin left in the Pen that you cannot inject. Do not transfer this to a syringe. Severe overdose can result.

Giving your injection

- Inject your insulin as your healthcare provider has shown you.
- Change (rotate) your injection sites within the area you choose for each dose to reduce your risk of getting lipodystrophy (pits in skin or thickened skin) and localized cutaneous amyloidosis (skin with lumps) at the injection sites.
- Do not use the exact same spot for each injection.
- Do not inject where the skin has pits, is thickened, or has lumps.
- Do not inject where the skin is tender, bruised, scaly or hard, or into scars or damaged skin.
- Do not try to change your dose while injecting.

Step 10:

- Choose your injection site.
  LYUMJEV is injected under the skin (subcutaneously) of your stomach area, buttocks, upper legs or upper arms.
- Wipe your skin with an alcohol swab, and let your skin dry before you inject your dose.

Step 11:

- Insert the needle into your skin.
- Push the dose knob all the way in.

- Continue to hold the dose knob in and slowly count to 5 before removing the needle.

Do not try to inject your insulin by turning the dose knob. You will not receive your insulin by turning the dose knob.

Step 12:

- Pull the needle out of your skin.
  - A drop of insulin at the needle tip is normal. It will not affect your dose.
- Check the number in the dose window.
  - If you see “0” in the dose window, you have received the full amount you dialed.
  - If you do not see “0” in the dose window, you did not receive your full dose. Do not redial. Insert the needle into your skin and finish your injection.
  - If you still do not think you received the full amount you dialed for your injection, do not start over or repeat that injection. Monitor your blood glucose as instructed by your healthcare provider.
  - If you normally need to give 2 injections for your full dose, be sure to give your second injection.

The plunger only moves a little with each injection, and you may not notice that it moves.
If you see blood after you take the needle out of your skin, press the injection site lightly with a piece of gauze or an alcohol swab. Do not rub the area.

After your injection

Step 13:

- Carefully replace the outer needle shield

Step 14:

- Unscrew the capped needle and throw it away (see Disposing of Pens and needles section).
- Do not store the Pen with the needle attached to prevent leaking, blocking the needle, and air from entering the Pen.

Step 15:

- Replace the Pen cap by lining up the cap clip with the dose indicator and pushing straight on.

Disposing of Pens and needles

- Put your used needles in a FDA-cleared sharps disposal container right away after use. Do not throw away (dispose of) loose needles in your household trash.
- If you do not have a FDA-cleared sharps disposal container, you may use a household container that is:
  - made of a heavy-duty plastic,
  - can be closed with a tight-fitting, puncture-resistant lid, without sharps being able to come out,
  - upright and stable during use,
  - leak-resistant, and
  - properly labeled to warn of hazardous waste inside the container.
- When your sharps disposal container is almost full, you will need to follow your community guidelines for the right way to dispose of your sharps disposal container. There may be state or local laws about how you should throw away used needles and syringes. For more information about safe sharps disposal, and for specific information about sharps disposal in the state that you live in, go to the FDA's website at: http://www.fda.gov/safesharpsdisposal
- Do not dispose of your used sharps disposal container in your household trash unless your community guidelines permit this. Do not recycle your used sharps disposal container.
- The used Pen may be discarded in your household trash after you have removed the needle.

Storing your Pen

Unused Pens

- Store unused Pens in the refrigerator at 36°F to 46°F (2°C to 8°C).
- Do not freeze LYUMJEV. Do not use if it has been frozen.
- Unused Pens may be used until the expiration date printed on the label if the Pen has been kept in the refrigerator.

In-use Pen

- Store the Pen you are currently using at room temperature [up to 86°F (30°C)]. Keep away from heat and light.
- Throw away the LYUMJEV KwikPen you are using after 28 days, even if it still has insulin left in it.

General information about the safe and effective use of your Pen

- Keep your Pen and needles out of the sight and reach of children.
- Do not use your Pen if any part looks broken or damaged.
- Always carry an extra Pen in case yours is lost or damaged.

Troubleshooting

- If you cannot remove the Pen cap, gently twist the cap back and forth, and then pull the cap straight off.
- If the dose knob is hard to push:
  - pushing the dose knob more slowly will make it easier to inject.
  - your needle may be blocked. Put on a new needle and prime the Pen.
  - you may have dust, food, or liquid inside the Pen. Throw the Pen away and get a new Pen.

If you have any questions or problems with your LYUMJEV KwikPen, contact Lilly at 1-800-545-5979 or call your healthcare provider for help. For more information on LYUMJEV KwikPen and insulin, go to www.lyumjev.com.

Scan this code to launch

www.lyumjev.com

This Instructions for Use has been approved by the U.S. Food and Drug Administration.

Manufactured by:
Eli Lilly and Company
Indianapolis, IN 46285, USA
US License Number 1891

LYUMJEV™ and LYUMJEV™ KwikPen® are trademarks of Eli Lilly and Company.

Copyright © 2020, Eli Lilly and Company. All rights reserved.

LYUMJEV KwikPen meets the current dose accuracy and functional requirements of ISO 11608-1.

Issued: June 2020

LUMKP200-0001-IFU-20200615

PACKAGE LABEL – LYUMJEV U100 Vial Carton

NDC 0002-7728-01

LYUMJEVTM

(insulin lispro-aabc)

injection

100 units per mL (U-100)

for subcutaneous or intravenous use

10 mL multiple-dose vial

Rx only

www.lyumjev.com

Lilly

PACKAGE LABEL – LYUMJEV U100 Cartridges 5 Count Carton

NDC 0002-7726-05

5 x 3 mL Cartridges

LYUMJEVTM

(insulin lispro-aabc)

injection

For Single Patient Use Only

100 units per mL (U-100)

For subcutaneous use

Rx only

For use in Eli Lilly and Company's HumaPen® LUXURA®HD and other compatible insulin delivery devices.

www.lyumjev.com

Lilly

PACKAGE LABEL – LYUMJEV U100 KwikPen 5 Count Carton

Dispense in this sealed carton.

NDC 0002-8207-05

LYUMJEVTM KwikPen®

(insulin lispro-aabc)

injection

For Single Patient Use Only

100 units per mL (U-100)

For subcutaneous use

5 x 3 mL prefilled pens

Rx only

Needles not included

This device is recommended for use with Becton, Dickinson and Company's insulin pen needles.

Lilly

PACKAGE LABEL

PACKAGE LABEL – LYUMJEV U100 Junior KwikPen 5 Count Carton

Dispense in this sealed carton.

NDC 0002-8351-05

LYUMJEVTM

Junior KwikPen®

(insulin lispro-aabc)

injection

For Single Patient Use Only

100 units per mL (U-100)

This pen can deliver 0.5 (1/2) to 30 units in one injection.

5 x 3 mL prefilled pens

For subcutaneous use

Rx only

Needles not included

This device is recommended for use with Becton, Dickinson and Company's insulin pen needles.

Lilly

PACKAGE LABEL

PACKAGE LABEL – LYUMJEV U100 Tempo Pen 5 Count Carton

Dispense in this sealed carton.

NDC 0002-8235-05

LYUMJEVTM Tempo PenTM

(insulin lispro-aabc)

injection

For Single Patient Use Only

100 units per mL (U-100)

For subcutaneous use

5 x 3 mL prefilled pens

Rx only

Needles not included

This device is recommended for use with Becton, Dickinson and Company's insulin pen needles.

Lilly

PACKAGE LABEL – LYUMJEV U200 KwikPen 5 Count Carton

Dispense in this sealed carton.

NDC 0002-8228-27

LYUMJEVTM KwikPen®

(insulin lispro-aabc)

injection

For Single Patient Use Only

200 units per mL (U-200)

For subcutaneous use

2 x 3 mL prefilled pens

Rx only

Needles not included

This device is recommended for use with Becton, Dickinson and Company's insulin pen needles.

Lilly

DO NOT TRANSFER TO A SYRINGE SEVERE OVERDOSE CAN RESULT